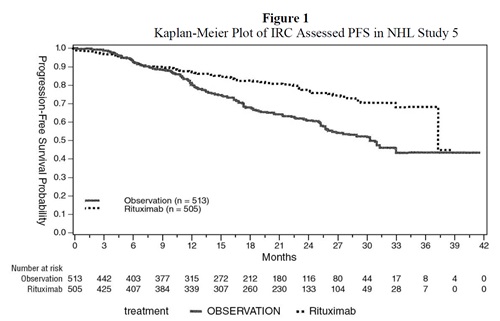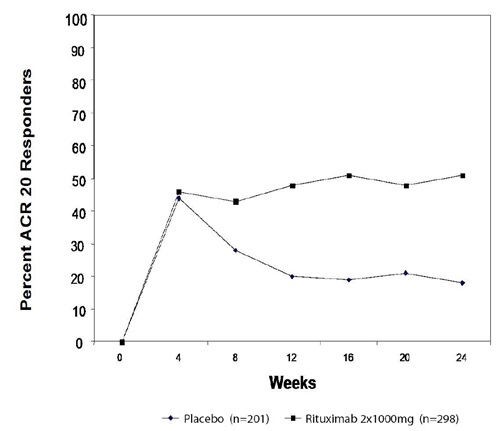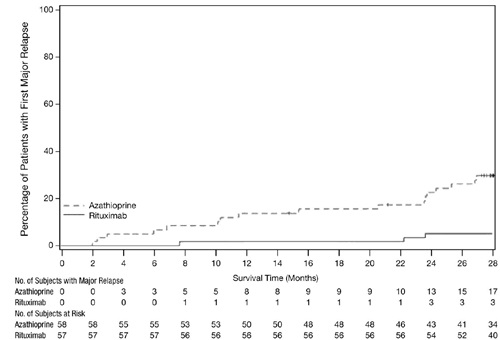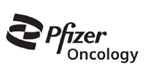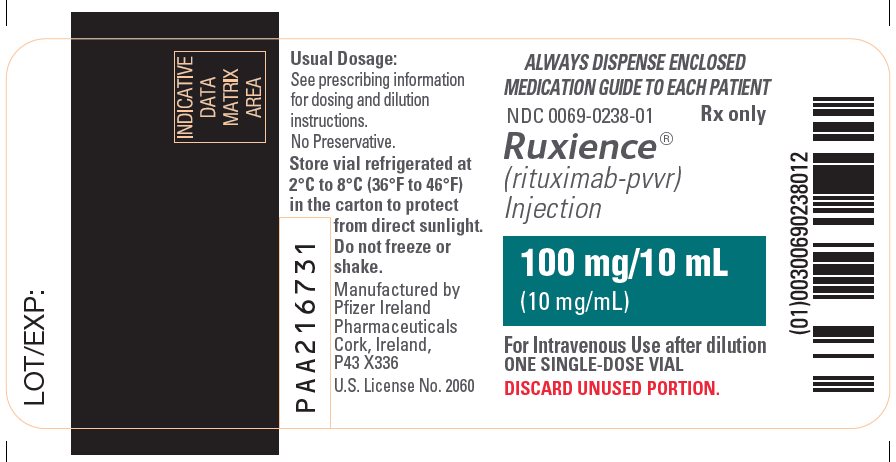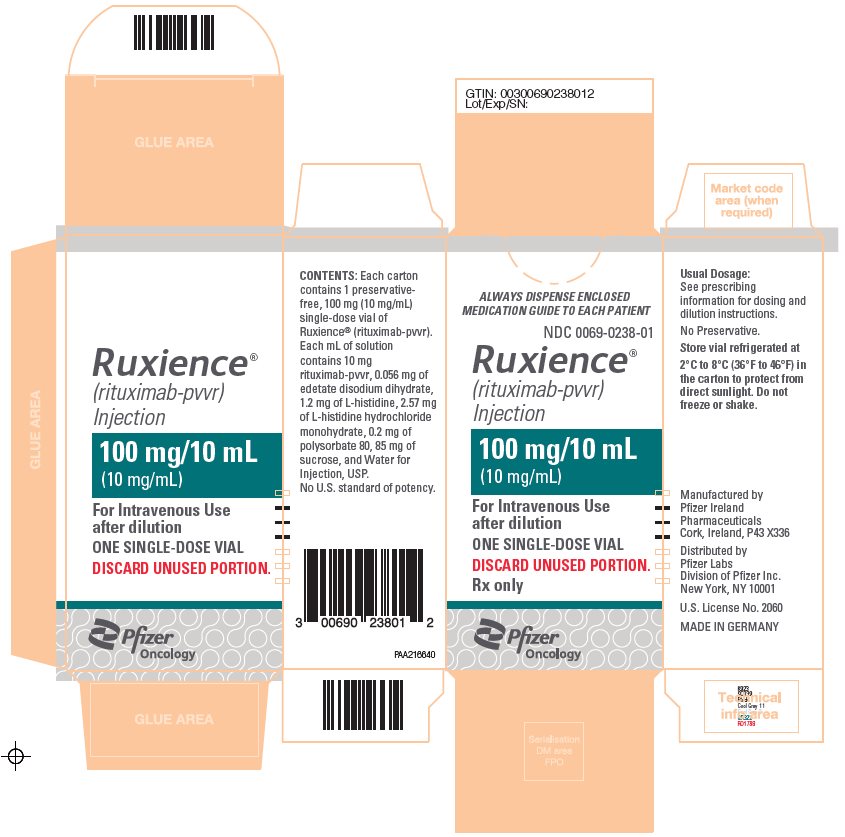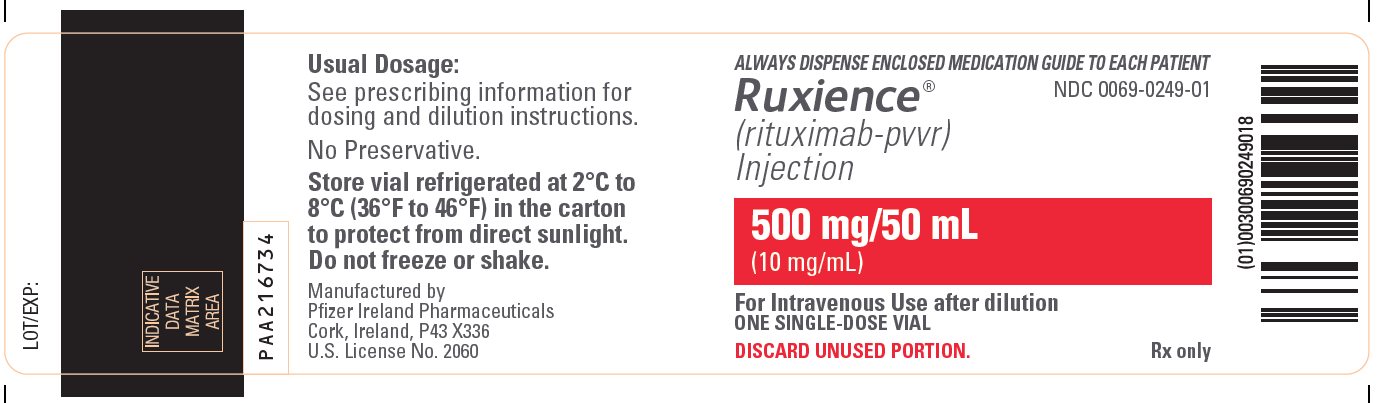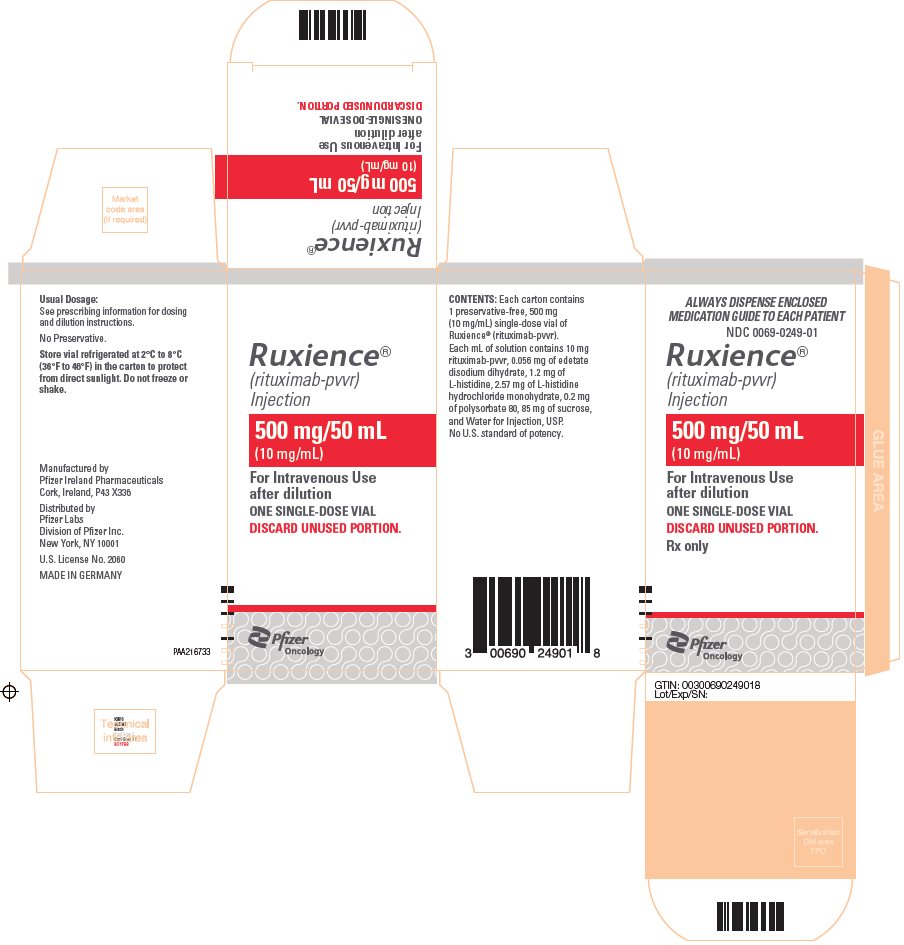 DRUG LABEL: Ruxience
NDC: 0069-0238 | Form: INJECTION, SOLUTION
Manufacturer: Pfizer Laboratories Div Pfizer Inc
Category: prescription | Type: HUMAN PRESCRIPTION DRUG LABEL
Date: 20250618

ACTIVE INGREDIENTS: RITUXIMAB 100 mg/10 mL
INACTIVE INGREDIENTS: EDETATE DISODIUM 25.7 mg/10 mL; POLYSORBATE 80 2 mg/10 mL; SUCROSE 850 mg/10 mL; WATER; HISTIDINE 12 mg/10 mL; HISTIDINE MONOHYDROCHLORIDE MONOHYDRATE 25.7 mg/10 mL

HIGHLIGHTS OF PRESCRIBING INFORMATION

These highlights do not include all the information needed to use RUXIENCE safely and effectively. See full prescribing information for RUXIENCE.
RUXIENCE® (rituximab-pvvr) injection, for intravenous use
Initial U.S. Approval: 2019
RUXIENCE (rituximab-pvvr) is biosimilar [Biosimilar means that the biological product is approved based on data demonstrating that it is highly similar to an FDA-approved biological product, known as a reference product, and that there are no clinically meaningful differences between the biosimilar product and the reference product. Biosimilarity of RUXIENCE has been demonstrated for the condition(s) of use (e.g., indication(s), dosing regimen(s)), strength(s), dosage form(s), and route(s) of administration described in its Full Prescribing Information.] to RITUXAN (rituximab)

RECENT MAJOR CHANGES

Indications and Usage, Pemphigus Vulgaris (PV) (1.5) | 6/2025
Dosage and Administration (2) | 6/2025
Warnings and Precautions (5) | 6/2025

WARNING: FATAL INFUSION-RELATED REACTIONS, SEVERE MUCOCUTANEOUS REACTIONS, HEPATITIS B VIRUS REACTIVATION and PROGRESSIVE MULTIFOCAL LEUKOENCEPHALOPATHY

See full prescribing information for complete boxed warning.

- Fatal infusion-related reactions within 24 hours of rituximab infusion; approximately 80% of fatal reactions occurred with first infusion. Monitor patients and discontinue RUXIENCE infusion for severe reactions (5.1, 6.1).
- Severe mucocutaneous reactions, some with fatal outcomes (5.2).
- Hepatitis B virus (HBV) reactivation, in some cases resulting in fulminant hepatitis, hepatic failure, and death (5.3).
- Progressive multifocal leukoencephalopathy (PML) resulting in death (5.4, 6.3).

1 INDICATIONS AND USAGE

RUXIENCE is a CD20-directed cytolytic antibody indicated for the treatment of:

- Adult patients with Non-Hodgkin's Lymphoma (NHL) (1.1).
  - Relapsed or refractory, low grade or follicular, CD20-positive B-cell NHL as a single agent.
  - Previously untreated follicular, CD20-positive, B-cell NHL in combination with first line chemotherapy and, in patients achieving a complete or partial response to a rituximab product in combination with chemotherapy, as single-agent maintenance therapy.
  - Non-progressing (including stable disease), low-grade, CD20-positive, B-cell NHL as a single agent after first-line cyclophosphamide, vincristine, and prednisone (CVP) chemotherapy.
  - Previously untreated diffuse large B-cell, CD20-positive NHL in combination with (cyclophosphamide, doxorubicin, vincristine, and prednisone) (CHOP) or other anthracycline-based chemotherapy regimens.
- Adult patients with Chronic Lymphocytic Leukemia (CLL) (1.2).
  - Previously untreated and previously treated CD20-positive CLL in combination with fludarabine and cyclophosphamide (FC).
- Rheumatoid Arthritis (RA) in combination with methotrexate in adult patients with moderately-to-severely-active RA who have inadequate response to one or more TNF antagonist therapies (1.3).
- Granulomatosis with Polyangiitis (GPA) (Wegener's Granulomatosis) and Microscopic Polyangiitis (MPA) in adult patients in combination with glucocorticoids (1.4).
- Moderate to severe Pemphigus Vulgaris (PV) in adult patients (1.5).

2 DOSAGE AND ADMINISTRATION

- Administer only as an intravenous infusion (2.1).
- Do not administer as an intravenous push or bolus (2.1).
- RUXIENCE should only be administered by a healthcare professional with appropriate medical support to manage severe infusion-related reactions that can be fatal if they occur (2.1).
- The dose for adult B-cell NHL is 375 mg/m^2 (2.2).
- The dose for CLL is 375 mg/m^2 in the first cycle and 500 mg/m^2 in Cycles 2–6, in combination with FC, administered every 28 days (2.3).
- The dose as a component of Zevalin® (ibritumomab tiuxetan) Therapeutic Regimen is 250 mg/m^2 (2.4).
- The dose for RA in combination with methotrexate is two-1,000 mg intravenous infusions separated by 2 weeks (one course) every 24 weeks or based on clinical evaluation, but not sooner than every 16 weeks. Methylprednisolone 100 mg intravenous or equivalent glucocorticoid is recommended 30 minutes prior to each infusion (2.5).
- The induction dose for adult patients with active GPA and MPA in combination with glucocorticoids is 375 mg/m^2 once weekly for 4 weeks. The follow up dose for adult patients with GPA and MPA who have achieved disease control with induction treatment, in combination with glucocorticoids is two 500 mg intravenous infusions separated by two weeks, followed by a 500 mg intravenous infusion every 6 months thereafter based on clinical evaluation (2.6).
- The dose for PV is two-1,000 mg intravenous infusions separated by 2 weeks in combination with a tapering course of glucocorticoids, then a 500 mg intravenous infusion at Month 12 and every 6 months thereafter or based on clinical evaluation. Dose upon relapse is a 1,000 mg intravenous infusion with considerations to resume or increase the glucocorticoid dose based on clinical evaluation. Subsequent infusions may be no sooner than 16 weeks after the previous infusion (2.7). Methylprednisolone 100 mg intravenous or equivalent glucocorticoid is recommended 30 minutes prior to each infusion (2.8).

3 DOSAGE FORMS AND STRENGTHS

Injection: 100 mg/10 mL (10 mg/mL) and 500 mg/50 mL (10 mg/mL) solution in single-dose vials (3).

4 CONTRAINDICATIONS

None (4).

5 WARNINGS AND PRECAUTIONS

- Tumor lysis syndrome: Administer aggressive intravenous hydration, anti-hyperuricemic agents, monitor renal function (5.5).
- Infections: Withhold RUXIENCE and institute appropriate anti-infective therapy (5.6).
- Cardiac adverse reactions: Discontinue infusions in case of serious or life-threatening events (5.7).
- Renal toxicity: Discontinue in patients with rising serum creatinine or oliguria (5.8).
- Bowel obstruction and perforation: Consider and evaluate for abdominal pain, vomiting, or related symptoms (5.9).
- Immunizations: Live virus vaccinations prior to or during RUXIENCE treatment are not recommended (5.10).
- Embryo-Fetal toxicity: Can cause fetal harm. Advise females of reproductive potential of the potential risk to a fetus and use of effective contraception (5.11).

6 ADVERSE REACTIONS

Most common adverse reactions in clinical trials were:

- NHL (greater than or equal to 25%): infusion-related reactions, fever, lymphopenia, chills, infection and asthenia (6.1).
- CLL (greater than or equal to 25%): infusion-related reactions and neutropenia (6.1).
- RA (greater than or equal to 10%): upper respiratory tract infection, nasopharyngitis, urinary tract infection, and bronchitis (other important adverse reactions include infusion-related reactions, serious infections, and cardiovascular events) (6.1).
- GPA and MPA (greater than or equal to 15%): infections, nausea, diarrhea, headache, muscle spasms, anemia, peripheral edema, infusion-related reactions (6.1).
- PV (greater than or equal to 15%): infusion-related reactions, depression, upper respiratory tract infection/nasopharyngitis, headache (other important adverse reactions include infections) (6.1).

To report SUSPECTED ADVERSE REACTIONS, contact Pfizer Inc. at 1-800-438-1985 or FDA at 1-800-FDA-1088 or www.fda.gov/medwatch.

7 DRUG INTERACTIONS

Renal toxicity when used in combination with cisplatin (5.8).

8 USE IN SPECIFIC POPULATIONS

- Lactation: Advise not to breastfeed (8.2).
- Geriatric Use: In CLL patients older than 70 years of age, exploratory analyses suggest no benefit with the addition of rituximab to FC (8.5).

FULL PRESCRIBING INFORMATION

WARNING: FATAL INFUSION-RELATED REACTIONS, SEVERE MUCOCUTANEOUS REACTIONS, HEPATITIS B VIRUS REACTIVATION and PROGRESSIVE MULTIFOCAL LEUKOENCEPHALOPATHY

Infusion-Related Reactions
Administration of rituximab products can result in serious, including fatal, infusion-related reactions. Deaths within 24 hours of rituximab infusion have occurred. Approximately 80% of fatal infusion-related reactions occurred in association with the first infusion. Monitor patients closely. Discontinue RUXIENCE infusion for severe reactions and provide medical treatment for Grade 3 or 4 infusion-related reactions [see Warnings and Precautions (5.1), Adverse Reactions (6.1)].

Severe Mucocutaneous Reactions
Severe, including fatal, mucocutaneous reactions can occur in patients receiving rituximab products [see Warnings and Precautions (5.2)].

Hepatitis B Virus (HBV) Reactivation
HBV reactivation can occur in patients treated with rituximab products, in some cases resulting in fulminant hepatitis, hepatic failure, and death. Screen all patients for HBV infection before treatment initiation, and monitor patients during and after treatment with RUXIENCE. Discontinue RUXIENCE and concomitant medications in the event of HBV reactivation [see Warnings and Precautions (5.3)].

Progressive Multifocal Leukoencephalopathy (PML)
Progressive Multifocal Leukoencephalopathy (PML), including fatal PML, can occur in patients receiving rituximab products [see Warnings and Precautions (5.4), Adverse Reactions (6.3)].

1 INDICATIONS AND USAGE

1.1 Non-Hodgkin's Lymphoma (NHL)

RUXIENCE is indicated for the treatment of adult patients with:

- Relapsed or refractory, low-grade or follicular, CD20-positive, B-cell NHL as a single agent.
- Previously untreated follicular, CD20-positive, B-cell NHL in combination with first line chemotherapy and, in patients achieving a complete or partial response to a rituximab product in combination with chemotherapy, as single-agent maintenance therapy.
- Non-progressing (including stable disease), low-grade, CD20-positive, B-cell NHL as a single agent after first-line cyclophosphamide, vincristine, and prednisone (CVP) chemotherapy.
- Previously untreated diffuse large B-cell, CD20-positive NHL in combination with cyclophosphamide, doxorubicin, vincristine, prednisone (CHOP) or other anthracycline-based chemotherapy regimens.

1.2 Chronic Lymphocytic Leukemia (CLL)

RUXIENCE, in combination with fludarabine and cyclophosphamide (FC), is indicated for the treatment of adult patients with previously untreated and previously treated CD20-positive CLL.

1.3 Rheumatoid Arthritis (RA)

RUXIENCE, in combination with methotrexate, is indicated for the treatment of adult patients with moderately-to-severely-active rheumatoid arthritis who have had an inadequate response to one or more Tumor Necrosis Factor (TNF) antagonist therapies.

1.4 Granulomatosis with Polyangiitis (GPA) (Wegener's Granulomatosis) and Microscopic Polyangiitis (MPA)

RUXIENCE, in combination with glucocorticoids, is indicated for the treatment of adult patients with Granulomatosis with Polyangiitis (GPA) (Wegener's Granulomatosis) and Microscopic Polyangiitis (MPA).

1.5 Pemphigus Vulgaris (PV)

RUXIENCE is indicated for the treatment of adult patients with moderate to severe pemphigus vulgaris.

2 DOSAGE AND ADMINISTRATION

2.1 Important Dosing Information

Administer only as an intravenous infusion [see Dosage and Administration (2.9)]. Do not administer as an intravenous push or bolus.

RUXIENCE should only be administered by a healthcare professional with appropriate medical support to manage severe infusion-related reactions that can be fatal if they occur [see Warnings and Precautions (5.1)].

Premedicate before each infusion [see Dosage and Administration (2.8)].

Prior to First Infusion

Screen all patients for HBV infection by measuring HBsAg and anti-HBc before initiating treatment with RUXIENCE [see Warnings and Precautions (5.3)]. Obtain complete blood counts (CBC) including platelets prior to the first dose.

During RUXIENCE Therapy

In patients with lymphoid malignancies, during treatment with RUXIENCE monotherapy, obtain complete blood counts (CBC) with differential and platelet counts prior to each RUXIENCE course. During treatment with RUXIENCE and chemotherapy, obtain CBC with differential and platelet counts at weekly to monthly intervals and more frequently in patients who develop cytopenias [see Adverse Reactions (6.1)]. In patients with RA, GPA or MPA, obtain CBC with differential and platelet counts at two to four month intervals during RUXIENCE therapy. Continue to monitor for cytopenias after final dose and until resolution.

- First Infusion
  Standard Infusion: Initiate infusion at a rate of 50 mg/hour. In the absence of infusion toxicity, increase infusion rate by 50 mg/hour increments every 30 minutes, to a maximum of 400 mg/hour.
- Subsequent Infusions
  Standard Infusion: Initiate infusion at a rate of 100 mg/hour. In the absence of infusion toxicity, increase rate by 100 mg/hour increments at 30-minute intervals, to a maximum of 400 mg/hour.
  For Previously Untreated Follicular NHL and DLBCL Adult Patients: If patients did not experience a Grade 3 or 4 infusion-related adverse event during Cycle 1, a 90-minute infusion can be administered in Cycle 2 with a glucocorticoid-containing chemotherapy regimen.
  Initiate at a rate of 20% of the total dose given in the first 30 minutes and the remaining 80% of the total dose given over the next 60 minutes. If the 90-minute infusion is tolerated in Cycle 2, the same rate can be used when administering the remainder of the treatment regimen (through Cycle 6 or 8).
  Patients who have clinically significant cardiovascular disease or who have a circulating lymphocyte count greater than or equal to 5,000/mm^3 before Cycle 2 should not be administered the 90-minute infusion [see Clinical Studies (14.4)].
- Interrupt the infusion or slow the infusion rate for infusion-related reactions [see Boxed Warning, Warnings and Precautions (5.1)]. Continue the infusion at one-half the previous rate upon improvement of symptoms.

2.2 Recommended Dose for Non-Hodgkin's Lymphoma (NHL)

The recommended dose is 375 mg/m^2 as an intravenous infusion according to the following schedules:

- Relapsed or Refractory, Low-Grade or Follicular, CD20-Positive, B-Cell NHL
  Administer once weekly for 4 or 8 doses.
- Retreatment for Relapsed or Refractory, Low-Grade or Follicular, CD20-Positive, B-Cell NHL
  Administer once weekly for 4 doses.
- Previously Untreated, Follicular, CD20-Positive, B-Cell NHL
  Administer on Day 1 of each cycle of chemotherapy for up to 8 doses. In patients with complete or partial response, initiate RUXIENCE maintenance eight weeks following completion of a rituximab product in combination with chemotherapy. Administer RUXIENCE as a single agent every 8 weeks for 12 doses.
- Non-progressing, Low-Grade, CD20-Positive, B-Cell NHL, after first-line CVP chemotherapy
  Following completion of 6–8 cycles of CVP chemotherapy, administer once weekly for 4 doses at 6-month intervals to a maximum of 16 doses.
- Diffuse Large B-Cell NHL
  Administer on Day 1 of each cycle of chemotherapy for up to 8 infusions.

2.3 Recommended Dose for Chronic Lymphocytic Leukemia (CLL)

The recommended dose is 375 mg/m^2 the day prior to the initiation of FC chemotherapy, then 500 mg/m^2 on Day 1 of Cycles 2–6 (every 28 days).

2.4 Recommended Dose as a Component of Zevalin® for Treatment of NHL

When used as part of the Zevalin therapeutic regimen, infuse 250 mg/m^2 in accordance with the Zevalin package insert. Refer to the Zevalin package insert for full prescribing information regarding the Zevalin therapeutic regimen.

2.5 Recommended Dose for Rheumatoid Arthritis (RA)

- Administer RUXIENCE as two-1,000 mg intravenous infusions separated by 2 weeks.
- Glucocorticoids administered as methylprednisolone 100 mg intravenous or its equivalent 30 minutes prior to each infusion are recommended to reduce the incidence and severity of infusion-related reactions.
- Subsequent courses should be administered every 24 weeks or based on clinical evaluation, but not sooner than every 16 weeks.
- RUXIENCE is given in combination with methotrexate.

2.6 Recommended Dose for Granulomatosis with Polyangiitis (GPA) (Wegener's Granulomatosis) and Microscopic Polyangiitis (MPA)

Induction Treatment of Adult Patients with Active GPA/MPA

- Administer RUXIENCE as a 375 mg/m^2 intravenous infusion once weekly for 4 weeks for patients with active GPA or MPA.
- Glucocorticoids administered as methylprednisolone 1,000 mg intravenously per day for 1 to 3 days followed by oral prednisone as per clinical practice. This regimen should begin within 14 days prior to or with the initiation of RUXIENCE and may continue during and after the 4 week induction course of RUXIENCE treatment.

Follow up Treatment of Adult Patients with GPA/MPA who have Achieved Disease Control with Induction Treatment

- Administer RUXIENCE as two 500 mg intravenous infusions separated by two weeks, followed by a 500 mg intravenous infusion every 6 months thereafter based on clinical evaluation.
- If induction treatment of active disease was with a rituximab product, initiate follow up treatment with RUXIENCE within 24 weeks after the last induction infusion with a rituximab product or based on clinical evaluation, but no sooner than 16 weeks after the last induction infusion with a rituximab product.
- If induction treatment of active disease was with other standard of care immunosuppressants, initiate RUXIENCE follow up treatment within the 4 week period that follows achievement of disease control.

2.7 Recommended Dose for Pemphigus Vulgaris (PV)

- Administer RUXIENCE as two-1,000 mg intravenous infusions separated by 2 weeks in combination with a tapering course of glucocorticoids.
- Maintenance treatment
  Administer RUXIENCE as a 500 mg intravenous infusion at Month 12 and every 6 months thereafter or based on clinical evaluation.
- Treatment of relapse
  Administer RUXIENCE as a 1,000 mg intravenous infusion on relapse, and consider resuming or increasing the glucocorticoid dose based on clinical evaluation.

Subsequent infusions of RUXIENCE may be administered no sooner than 16 weeks following the previous infusion.

2.8 Recommended Dose for Premedication and Prophylactic Medications

Premedicate with acetaminophen and an antihistamine before each infusion of RUXIENCE. For adult patients administered RUXIENCE according to the 90-minute infusion rate, the glucocorticoid component of their chemotherapy regimen should be administered prior to infusion [see Clinical Studies (14.4)].

For RA, GPA and MPA, and PV patients, methylprednisolone 100 mg intravenously or its equivalent is recommended 30 minutes prior to each infusion.

Provide prophylaxis treatment for Pneumocystis jirovecii pneumonia (PCP) and herpes virus infections for patients with CLL during treatment and for up to 12 months following treatment as appropriate [see Warnings and Precautions (5.6)].

PCP prophylaxis is also recommended for patients with GPA and MPA during treatment and for at least 6 months following the last RUXIENCE infusion.

PCP prophylaxis should be considered for patients with PV during and following RUXIENCE treatment.

2.9 Administration and Storage

Use appropriate aseptic technique. Parenteral drug products should be inspected visually for particulate matter and discoloration prior to administration. RUXIENCE should be a clear to slightly opalescent, colorless to pale brownish-yellow liquid. Do not use vial if particulates or discoloration is present.

Administration

Use a sterile needle and syringe to prepare RUXIENCE. Withdraw the necessary amount of RUXIENCE and dilute to a final concentration of 1 mg/mL to 4 mg/mL in an infusion bag containing either 0.9% Sodium Chloride Injection or 5% Dextrose Injection. Gently invert the bag to mix the solution. Do not mix or dilute with other drugs. Discard any unused portion left in the vial.

Storage

If not used immediately, store diluted RUXIENCE solutions as shown in the table below.

Diluted RUXIENCE Solution Storage Conditions
Diluent Used to Prepare Solution for Infusion | Diluted RUXIENCE Solution Storage Conditions
0.9% Sodium Chloride Injection, USP | Store RUXIENCE solution diluted in 0.9% Sodium Chloride Injection, USP refrigerated at 2°C to 8°C (36°F to 46°F) for up to 16 days after preparation.
5% Dextrose Injection, USP | Store RUXIENCE solution diluted in 5% Dextrose Injection, USP refrigerated at 2°C to 8°C (36°F to 46°F) for up to 24 hours after preparation.

No incompatibilities between RUXIENCE and polyvinylchloride bags have been observed.

3 DOSAGE FORMS AND STRENGTHS

Injection: RUXIENCE is a clear to slightly opalescent, colorless to pale brownish-yellow solution for intravenous infusion:

- 100 mg/10 mL (10 mg/mL) in a single-dose vial
- 500 mg/50 mL (10 mg/mL) in a single-dose vial

4 CONTRAINDICATIONS

None.

5 WARNINGS AND PRECAUTIONS

5.1 Infusion-Related Reactions

Rituximab products can cause severe, including fatal, infusion-related reactions. Severe reactions typically occurred during the first infusion with time to onset of 30 to 120 minutes. Rituximab product-induced infusion-related reactions and sequelae include urticaria, hypotension, angioedema, hypoxia, bronchospasm, pulmonary infiltrates, acute respiratory distress syndrome, myocardial infarction, ventricular fibrillation, cardiogenic shock, anaphylactoid events, or death.

Premedicate patients with an antihistamine and acetaminophen prior to dosing. For RA, GPA and MPA, and PV patients, methylprednisolone 100 mg intravenously or its equivalent is recommended 30 minutes prior to each infusion. Institute medical management (e.g., glucocorticoids, epinephrine, bronchodilators, or oxygen) for infusion-related reactions as needed. Depending on the severity of the infusion-related reaction and the required interventions, temporarily or permanently discontinue RUXIENCE. Resume infusion at a minimum 50% reduction in rate after symptoms have resolved. Closely monitor the following patients: those with pre-existing cardiac or pulmonary conditions, those who experienced prior cardiopulmonary adverse reactions, and those with high numbers of circulating malignant cells (greater than or equal to 25,000/mm^3) [see Warnings and Precautions (5.7), Adverse Reactions (6.1)].

5.2 Severe Mucocutaneous Reactions

Mucocutaneous reactions, some with fatal outcome, can occur in patients treated with rituximab products. These reactions include paraneoplastic pemphigus, Stevens-Johnson syndrome, lichenoid dermatitis, vesiculobullous dermatitis, and toxic epidermal necrolysis. The onset of these reactions has been variable and includes reports with onset on the first day of rituximab exposure. Discontinue RUXIENCE in patients who experience a severe mucocutaneous reaction. The safety of re-administration of rituximab products to patients with severe mucocutaneous reactions has not been determined.

5.3 Hepatitis B Virus (HBV) Reactivation

Hepatitis B virus (HBV) reactivation, in some cases resulting in fulminant hepatitis, hepatic failure, and death, can occur in patients treated with drugs classified as CD20-directed cytolytic antibodies, including rituximab products. Cases have been reported in patients who are hepatitis B surface antigen (HBsAg) positive and also in patients who are HBsAg negative but are hepatitis B core antibody (anti-HBc) positive. Reactivation also has occurred in patients who appear to have resolved hepatitis B infection (i.e., HBsAg negative, anti-HBc positive and hepatitis B surface antibody [anti-HBs] positive).

HBV reactivation is defined as an abrupt increase in HBV replication manifesting as a rapid increase in serum HBV DNA levels or detection of HBsAg in a person who was previously HBsAg negative and anti-HBc positive. Reactivation of HBV replication is often followed by hepatitis, i.e., increase in transaminase levels. In severe cases increase in bilirubin levels, liver failure, and death can occur.

Screen all patients for HBV infection by measuring HBsAg and anti-HBc before initiating treatment with RUXIENCE. For patients who show evidence of prior hepatitis B infection (HBsAg positive [regardless of antibody status] or HBsAg negative but anti-HBc positive), consult with physicians with expertise in managing hepatitis B regarding monitoring and consideration for HBV antiviral therapy before and/or during RUXIENCE treatment.

Monitor patients with evidence of current or prior HBV infection for clinical and laboratory signs of hepatitis or HBV reactivation during and for several months following RUXIENCE therapy. HBV reactivation has been reported up to 24 months following completion of rituximab therapy.

In patients who develop reactivation of HBV while on RUXIENCE, immediately discontinue RUXIENCE and any concomitant chemotherapy, and institute appropriate treatment. Insufficient data exist regarding the safety of resuming RUXIENCE treatment in patients who develop HBV reactivation. Resumption of RUXIENCE treatment in patients whose HBV reactivation resolves should be discussed with physicians with expertise in managing HBV.

5.4 Progressive Multifocal Leukoencephalopathy (PML)

JC virus infection resulting in PML and death can occur in rituximab product-treated patients with hematologic malignancies or with autoimmune diseases. The majority of patients with hematologic malignancies diagnosed with PML received rituximab in combination with chemotherapy or as part of a hematopoietic stem cell transplant. The patients with autoimmune diseases had prior or concurrent immunosuppressive therapy. Most cases of PML were diagnosed within 12 months of their last infusion of rituximab.

Consider the diagnosis of PML in any patient presenting with new-onset neurologic manifestations. Evaluation of PML includes, but is not limited to, consultation with a neurologist, brain MRI, and lumbar puncture.

Discontinue RUXIENCE and consider discontinuation or reduction of any concomitant chemotherapy or immunosuppressive therapy in patients who develop PML.

5.5 Tumor Lysis Syndrome (TLS)

Acute renal failure, hyperkalemia, hypocalcemia, hyperuricemia, or hyperphosphatemia from tumor lysis, sometimes fatal, can occur within 12–24 hours after the first infusion of rituximab products in patients with NHL. A high number of circulating malignant cells (greater than or equal to 25,000/mm^3) or high tumor burden, confers a greater risk of TLS.

Administer aggressive intravenous hydration and anti-hyperuricemic therapy in patients at high risk for TLS. Correct electrolyte abnormalities, monitor renal function and fluid balance, and administer supportive care, including dialysis as indicated [see Warnings and Precautions (5.8)].

5.6 Infections

Serious, including fatal, bacterial, fungal, and new or reactivated viral infections can occur during and following the completion of rituximab product-based therapy. Infections have been reported in some patients with prolonged hypogammaglobulinemia (defined as hypogammaglobulinemia greater than 11 months after rituximab exposure). New or reactivated viral infections included cytomegalovirus, herpes simplex virus, parvovirus B19, varicella zoster virus, West Nile virus, and hepatitis B and C. Discontinue RUXIENCE for serious infections and institute appropriate anti-infective therapy [see Adverse Reactions (6.1, 6.3)]. RUXIENCE is not recommended for use in patients with severe, active infections.

5.7 Cardiovascular Adverse Reactions

Cardiac adverse reactions, including ventricular fibrillation, myocardial infarction, and cardiogenic shock may occur in patients receiving rituximab products. Discontinue infusions for serious or life-threatening cardiac arrhythmias. Perform cardiac monitoring during and after all infusions of RUXIENCE for patients who develop clinically significant arrhythmias, or who have a history of arrhythmia or angina [see Adverse Reactions (6.1)].

5.8 Renal Toxicity

Severe, including fatal, renal toxicity can occur after rituximab product administration in patients with NHL. Renal toxicity has occurred in patients who experience tumor lysis syndrome and in patients with NHL administered concomitant cisplatin therapy during clinical trials. The combination of cisplatin and RUXIENCE is not an approved treatment regimen. Monitor closely for signs of renal failure and discontinue RUXIENCE in patients with a rising serum creatinine or oliguria [see Warnings and Precautions (5.5)].

5.9 Bowel Obstruction and Perforation

Abdominal pain, bowel obstruction and perforation, in some cases leading to death, can occur in patients receiving rituximab products in combination with chemotherapy. In postmarketing reports, the mean time to documented gastrointestinal perforation was 6 (range 1–77) days in patients with NHL. Evaluate if symptoms of obstruction such as abdominal pain or repeated vomiting occur.

5.10 Immunization

The safety of immunization with live viral vaccines following rituximab product therapy has not been studied and vaccination with live virus vaccines is not recommended before or during treatment.

For patients treated with RUXIENCE, physicians should review the patient's vaccination status and patients should, if possible, be brought up-to-date with all immunizations in agreement with current immunization guidelines prior to initiating RUXIENCE and administer non live vaccines at least 4 weeks prior to a course of RUXIENCE.

The effect of rituximab on immune responses was assessed in a randomized, controlled study in patients with RA treated with rituximab and methotrexate (MTX) compared to patients treated with MTX alone.

A response to pneumococcal vaccination (a T-cell independent antigen) as measured by an increase in antibody titers to at least 6 of 12 serotypes was lower in patients treated with rituximab plus MTX as compared to patients treated with MTX alone (19% vs. 61%). A lower proportion of patients in the rituximab plus MTX group developed detectable levels of anti-keyhole limpet hemocyanin antibodies (a novel protein antigen) after vaccination compared to patients on MTX alone (47% vs. 93%).

A positive response to tetanus toxoid vaccine (a T-cell dependent antigen with existing immunity) was similar in patients treated with rituximab plus MTX compared to patients on MTX alone (39% vs. 42%). The proportion of patients maintaining a positive Candida skin test (to evaluate delayed type hypersensitivity) was also similar (77% of patients on rituximab plus MTX vs. 70% of patients on MTX alone).

Most patients in the rituximab-treated group had B-cell counts below the lower limit of normal at the time of immunization. The clinical implications of these findings are not known.

5.11 Embryo-Fetal Toxicity

Based on human data, rituximab products can cause fetal harm due to B-cell lymphocytopenia in infants exposed in-utero. Advise pregnant women of the potential risk to a fetus. Advise females of reproductive potential to use effective contraception while receiving RUXIENCE and for 12 months after the last dose [see Use in Specific Populations (8.1, 8.3)].

5.12 Concomitant Use with Other Biologic Agents and DMARDS other than Methotrexate in RA, GPA and MPA, PV

Limited data are available on the safety of the use of biologic agents or disease modifying anti-rheumatic drugs (DMARDs) other than methotrexate in RA patients exhibiting peripheral B-cell depletion following treatment with rituximab. Observe patients closely for signs of infection if biologic agents and/or DMARDs are used concomitantly. Use of concomitant immunosuppressants other than corticosteroids has not been studied in GPA or MPA or PV patients exhibiting peripheral B-cell depletion following treatment with rituximab products.

5.13 Use in RA Patients Who Have Not Had Prior Inadequate Response to Tumor Necrosis Factor (TNF) Antagonists

While the efficacy of rituximab was supported in four controlled trials in patients with RA with prior inadequate responses to non-biologic DMARDs, and in a controlled trial in MTX-naïve patients, a favorable risk-benefit relationship has not been established in these populations. The use of RUXIENCE in patients with RA who have not had prior inadequate response to one or more TNF antagonists is not recommended [see Clinical Studies (14.6)].

6 ADVERSE REACTIONS

The following clinically significant adverse reactions are discussed in greater detail in other sections of the labeling:

- Infusion-related reactions [see Warnings and Precautions (5.1)]
- Severe mucocutaneous reactions [see Warnings and Precautions (5.2)]
- Hepatitis B reactivation with fulminant hepatitis [see Warnings and Precautions (5.3)]
- Progressive multifocal leukoencephalopathy [see Warnings and Precautions (5.4)]
- Tumor lysis syndrome [see Warnings and Precautions (5.5)]
- Infections [see Warnings and Precautions (5.6)]
- Cardiovascular adverse reactions [see Warnings and Precautions (5.7)]
- Renal toxicity [see Warnings and Precautions (5.8)]
- Bowel obstruction and perforation [see Warnings and Precautions (5.9)]

6.1 Clinical Trials Experience

Because clinical trials are conducted under widely varying conditions, adverse reaction rates observed in the clinical trials of a drug cannot be directly compared to rates in the clinical trials of another drug and may not reflect the rates observed in clinical practice.

B-Cell Malignancies

The data described below reflect exposure to rituximab in 3,092 patients, with exposures ranging from a single infusion up to 2 years. Rituximab was studied in both single-arm and controlled trials (n=356 and n=2,427). The population included 1,180 patients with low grade or follicular lymphoma, 927 patients with DLBCL, 676 patients with CLL, and 309 patients with another indication. Most NHL patients received rituximab as an infusion of 375 mg/m^2 per infusion, given as a single agent weekly for up to 8 doses, in combination with chemotherapy for up to 8 doses, or following chemotherapy for up to 16 doses. CLL patients received rituximab 375 mg/m^2 as an initial infusion followed by 500 mg/m^2 for up to 5 doses, in combination with fludarabine and cyclophosphamide. Seventy-one percent of CLL patients received 6 cycles and 90% received at least 3 cycles of rituximab-based therapy.

The most common adverse reactions of rituximab (incidence greater than or equal to 25%) observed in clinical trials of patients with NHL were infusion-related reactions, fever, lymphopenia, chills, infection, and asthenia.

The most common adverse reactions of rituximab (incidence greater than or equal to 25%) observed in clinical trials of patients with CLL were: infusion-related reactions and neutropenia.

Infusion-Related Reactions
In the majority of patients with NHL, infusion-related reactions consisting of fever, chills/rigors, nausea, pruritus, angioedema, hypotension, headache, bronchospasm, urticaria, rash, vomiting, myalgia, dizziness, or hypertension occurred during the first rituximab infusion. Infusion-related reactions typically occurred within 30 to 120 minutes of beginning the first infusion and resolved with slowing or interruption of the rituximab infusion and with supportive care (diphenhydramine, acetaminophen, and intravenous saline). The incidence of infusion-related reactions was highest during the first infusion (77%) and decreased with each subsequent infusion [see Warnings and Precautions (5.1)]. In adult patients with previously untreated follicular NHL or previously untreated DLBCL, who did not experience a Grade 3 or 4 infusion-related reaction in Cycle 1 and received a 90-minute infusion of rituximab at Cycle 2, the incidence of Grade 3–4 infusion-related reactions on the day of, or day after the infusion was 1.1% (95% CI [0.3%, 2.8%]). For Cycles 2–8, the incidence of Grade 3–4 infusion-related reactions on the day of or day after the 90-minute infusion, was 2.8% (95% CI [1.3%, 5.0%]) [see Warnings and Precautions (5.1), Clinical Studies (14.4)].

Infections
Serious infections (NCI CTCAE Grade 3 or 4), including sepsis, occurred in less than 5% of patients with NHL in the single-arm studies. The overall incidence of infections was 31% (bacterial 19%, viral 10%, unknown 6%, and fungal 1%) [see Warnings and Precautions (5.6)].

In randomized, controlled studies where rituximab was administered following chemotherapy for the treatment of follicular or low-grade NHL, the rate of infection was higher among patients who received rituximab. In diffuse large B-cell lymphoma patients, viral infections occurred more frequently in those who received rituximab.

Cytopenias and Hypogammaglobulinemia
In patients with NHL receiving rituximab monotherapy, NCI-CTC Grade 3 and 4 cytopenias were reported in 48% of patients. These included lymphopenia (40%), neutropenia (6%), leukopenia (4%), anemia (3%), and thrombocytopenia (2%). The median duration of lymphopenia was 14 days (range, 1–588 days) and of neutropenia was 13 days (range, 2–116 days). A single occurrence of transient aplastic anemia (pure red cell aplasia) and two occurrences of hemolytic anemia following rituximab therapy occurred during the single-arm studies.

In studies of monotherapy, rituximab-induced B-cell depletion occurred in 70% to 80% of patients with NHL. Decreased IgM and IgG serum levels occurred in 14% of these patients.

In CLL trials, the frequency of prolonged neutropenia and late-onset neutropenia was higher in patients treated with rituximab in combination with fludarabine and cyclophosphamide (R-FC) compared to patients treated with FC. Prolonged neutropenia is defined as Grade 3–4 neutropenia that has not resolved between 24 and 42 days after the last dose of study treatment. Late-onset neutropenia is defined as Grade 3–4 neutropenia starting at least 42 days after the last treatment dose.

In patients with previously untreated CLL, the frequency of prolonged neutropenia was 8.5% for patients who received R-FC (n=402) and 5.8% for patients who received FC (n=398). In patients who did not have prolonged neutropenia, the frequency of late-onset neutropenia was 14.8% of 209 patients who received R-FC and 4.3% of 230 patients who received FC.

For patients with previously treated CLL, the frequency of prolonged neutropenia was 24.8% for patients who received R-FC (n=274) and 19.1% for patients who received FC (n=274). In patients who did not have prolonged neutropenia, the frequency of late-onset neutropenia was 38.7% in 160 patients who received R-FC and 13.6% of 147 patients who received FC.

Relapsed or Refractory, Low-Grade NHL
Adverse reactions presented in Table 1 occurred in 356 patients with relapsed or refractory, low-grade or follicular, CD20-positive, B-cell NHL treated in single-arm studies of rituximab administered as a single agent [see Clinical Studies (14.1)]. Most patients received rituximab 375 mg/m^2 weekly for 4 doses.

Table 1 Incidence of Adverse Reactions in Greater than or Equal to 5% of Patients with Relapsed or Refractory, Low-Grade or Follicular NHL, Receiving Single-agent Rituximab (N=356) [Adverse reactions observed up to 12 months following rituximab.] , [Adverse reactions graded for severity by NCI-CTC criteria.]
 | All Grades (%) | Grade 3 and 4 (%)
Any Adverse Reactions | 99 | 57
Body as a Whole | 86 | 10
Fever | 53 | 1
Chills | 33 | 3
Infection | 31 | 4
Asthenia | 26 | 1
Headache | 19 | 1
Abdominal Pain | 14 | 1
Pain | 12 | 1
Back Pain | 10 | 1
Throat Irritation | 9 | 0
Flushing | 5 | 0
Heme and Lymphatic System | 67 | 48
Lymphopenia | 48 | 40
Leukopenia | 14 | 4
Neutropenia | 14 | 6
Thrombocytopenia | 12 | 2
Anemia | 8 | 3
Skin and Appendages | 44 | 2
Night Sweats | 15 | 1
Rash | 15 | 1
Pruritus | 14 | 1
Urticaria | 8 | 1
Respiratory System | 38 | 4
Increased Cough | 13 | 1
Rhinitis | 12 | 1
Bronchospasm | 8 | 1
Dyspnea | 7 | 1
Sinusitis | 6 | 0
Metabolic and Nutritional Disorders | 38 | 3
Angioedema | 11 | 1
Hyperglycemia | 9 | 1
Peripheral Edema | 8 | 0
LDH Increase | 7 | 0
Digestive System | 37 | 2
Nausea | 23 | 1
Diarrhea | 10 | 1
Vomiting | 10 | 1
Nervous System | 32 | 1
Dizziness | 10 | 1
Anxiety | 5 | 1
Musculoskeletal System | 26 | 3
Myalgia | 10 | 1
Arthralgia | 10 | 1
Cardiovascular System | 25 | 3
Hypotension | 10 | 1
Hypertension | 6 | 1

In these single-arm rituximab studies, bronchiolitis obliterans occurred during and up to 6 months after rituximab infusion.

Previously Untreated, Low-Grade or Follicular, NHL
In NHL Study 4, patients in the R-CVP arm experienced a higher incidence of infusional toxicity and neutropenia compared to patients in the CVP arm. The following adverse reactions occurred more frequently (greater than or equal to 5%) in patients receiving R-CVP compared to CVP alone: rash (17% vs. 5%), cough (15% vs. 6%), flushing (14% vs. 3%), rigors (10% vs. 2%), pruritus (10% vs. 1%), neutropenia (8% vs. 3%), and chest tightness (7% vs. 1%) [see Clinical Studies (14.2)].

In NHL Study 5, detailed safety data collection was limited to serious adverse reactions, Grade greater than or equal to 2 infections, and Grade greater than or equal to 3 adverse reactions. In patients receiving rituximab as single-agent maintenance therapy following rituximab plus chemotherapy, infections were reported more frequently compared to the observation arm (37% vs. 22%). Grade 3-4 adverse reactions occurring at a higher incidence (greater than or equal to 2%) in the rituximab group were infections (4% vs. 1%) and neutropenia (4% vs. less than 1%).

In NHL Study 6, the following adverse reactions were reported more frequently (greater than or equal to 5%) in patients receiving rituximab following CVP compared to patients who received no further therapy: fatigue (39% vs. 14%), anemia (35% vs. 20%), peripheral sensory neuropathy (30% vs. 18%), infections (19% vs. 9%), pulmonary toxicity (18% vs. 10%), hepato-biliary toxicity (17% vs. 7%), rash and/or pruritus (17% vs. 5%), arthralgia (12% vs. 3%), and weight gain (11% vs. 4%). Neutropenia was the only Grade 3 or 4 adverse reaction that occurred more frequently (greater than or equal to 2%) in the rituximab arm compared with those who received no further therapy (4% vs. 1%) [see Clinical Studies (14.3)].

DLBCL
In NHL Studies 7 (NCT00003150) and 8, [see Clinical Studies (14.3)], the following adverse reactions, regardless of severity, were reported more frequently (greater than or equal to 5%) in patients age greater than or equal to 60 years receiving R-CHOP as compared to CHOP alone: pyrexia (56% vs. 46%), lung disorder (31% vs. 24%), cardiac disorder (29% vs. 21%), and chills (13% vs. 4%). Detailed safety data collection in these studies was primarily limited to Grade 3 and 4 adverse reactions and serious adverse reactions.

In NHL Study 8, a review of cardiac toxicity determined that supraventricular arrhythmias or tachycardia accounted for most of the difference in cardiac disorders (4.5% for R-CHOP vs. 1.0% for CHOP).

The following Grade 3 or 4 adverse reactions occurred more frequently among patients in the R-CHOP arm compared with those in the CHOP arm: thrombocytopenia (9% vs. 7%) and lung disorder (6% vs. 3%). Other Grade 3 or 4 adverse reactions occurring more frequently among patients receiving R-CHOP were viral infection (NHL Study 8), neutropenia (NHL Studies 8 and 9 (NCT00064116)), and anemia (NHL Study 9).

CLL

The data below reflect exposure to rituximab in combination with fludarabine and cyclophosphamide in 676 patients with CLL in CLL Study 1 (NCT00281918) or CLL Study 2 (NCT00090051) [see Clinical Studies (14.5)]. The age range was 30–83 years and 71% were men. Detailed safety data collection in CLL Study 1 was limited to Grade 3 and 4 adverse reactions and serious adverse reactions.

Infusion-related adverse reactions were defined by any of the following adverse events occurring during or within 24 hours of the start of infusion: nausea, pyrexia, chills, hypotension, vomiting, and dyspnea.

In CLL Study 1, the following Grade 3 and 4 adverse reactions occurred more frequently in R-FC-treated patients compared to FC-treated patients: infusion-related reactions (9% in R-FC arm), neutropenia (30% vs. 19%), febrile neutropenia (9% vs. 6%), leukopenia (23% vs. 12%), and pancytopenia (3% vs. 1%).

In CLL Study 2, the following Grade 3 or 4 adverse reactions occurred more frequently in R-FC-treated patients compared to FC-treated patients: infusion-related reactions (7% in R-FC arm), neutropenia (49% vs. 44%), febrile neutropenia (15% vs. 12%), thrombocytopenia (11% vs. 9%), hypotension (2% vs. 0%), and hepatitis B (2% vs. less than 1%). Fifty-nine percent of R-FC-treated patients experienced an infusion-related reaction of any severity.

Rheumatoid Arthritis

The data presented below reflect the experience in 2,578 RA patients treated with rituximab in controlled and long-term studies [Pooled studies: NCT00074438, NCT00422383, NCT00468546, NCT00299130, NCT00282308, NCT00266227, NCT02693210, NCT02093026 and NCT02097745.] with a total exposure of 5,014 patient-years.

Among all exposed patients, adverse reactions reported in greater than 10% of patients include infusion-related reactions, upper respiratory tract infection, nasopharyngitis, urinary tract infection, and bronchitis.

In placebo-controlled studies, patients received 2 × 500 mg or 2 × 1,000 mg intravenous infusions of rituximab or placebo, in combination with methotrexate, during a 24-week period. From these studies, 938 patients treated with rituximab (2 × 1,000 mg) or placebo have been pooled (see Table 2). Adverse reactions reported in greater than or equal to 5% of patients were hypertension, nausea, upper respiratory tract infection, arthralgia, pyrexia and pruritus (see Table 2). The rates and types of adverse reactions in patients who received rituximab 2 × 500 mg were similar to those observed in patients who received rituximab 2 × 1,000 mg.

Table 2 [These data are based on 938 patients treated in Phase 2 and 3 studies of rituximab (2 × 1,000 mg) or placebo administered in combination with methotrexate.] Incidence of All Adverse Reactions [Coded using MedDRA.] Occurring in Greater than or Equal to 2% and at Least 1% Greater than Placebo Among Rheumatoid Arthritis Patients in Clinical Studies Up to Week 24 (Pooled)
Adverse Reaction | Placebo + MTX N=398 n (%) | Rituximab + MTX N=540 n (%)
Hypertension | 21 (5) | 43 (8)
Nausea | 19 (5) | 41 (8)
Upper Respiratory Tract Infection | 23 (6) | 37 (7)
Arthralgia | 14 (4) | 31 (6)
Pyrexia | 8 (2) | 27 (5)
Pruritus | 5 (1) | 26 (5)
Chills | 9 (2) | 16 (3)
Dyspepsia | 3 (<1) | 16 (3)
Rhinitis | 6 (2) | 14 (3)
Paresthesia | 3 (<1) | 12 (2)
Urticaria | 3 (<1) | 12 (2)
Abdominal Pain Upper | 4 (1) | 11 (2)
Throat Irritation | 0 (0) | 11 (2)
Anxiety | 5 (1) | 9 (2)
Migraine | 2 (<1) | 9 (2)
Asthenia | 1 (<1) | 9 (2)

Infusion-Related Reactions
In the rituximab RA pooled placebo-controlled studies, 32% of rituximab-treated patients experienced an adverse reaction during or within 24 hours following their first infusion, compared to 23% of placebo-treated patients receiving their first infusion. The incidence of adverse reactions during the 24-hour period following the second infusion, rituximab or placebo, decreased to 11% and 13%, respectively. Acute infusion-related reactions (manifested by fever, chills, rigors, pruritus, urticaria/rash, angioedema, sneezing, throat irritation, cough, and/or bronchospasm, with or without associated hypotension or hypertension) were experienced by 27% of rituximab-treated patients following their first infusion, compared to 19% of placebo-treated patients receiving their first placebo infusion. The incidence of these acute infusion-related reactions following the second infusion of rituximab or placebo decreased to 9% and 11%, respectively. Serious acute infusion-related reactions were experienced by less than 1% of patients in either treatment group. Acute infusion-related reactions required dose modification (stopping, slowing, or interruption of the infusion) in 10% and 2% of patients receiving rituximab or placebo, respectively, after the first course. The proportion of patients experiencing acute infusion-related reactions decreased with subsequent courses of rituximab. The administration of intravenous glucocorticoids prior to rituximab infusions reduced the incidence and severity of such reactions, however, there was no clear benefit from the administration of oral glucocorticoids for the prevention of acute infusion-related reactions. Patients in clinical studies also received antihistamines and acetaminophen prior to rituximab infusions.

Infections
In the pooled, placebo-controlled studies, 39% of patients in the rituximab group experienced an infection of any type compared to 34% of patients in the placebo group. The most common infections were nasopharyngitis, upper respiratory tract infections, urinary tract infections, bronchitis, and sinusitis.

The incidence of serious infections was 2% in the rituximab-treated patients and 1% in the placebo group.

In the experience with rituximab in 2,578 RA patients, the rate of serious infections was 4.31 per 100 patient-years. The most common serious infections (greater than or equal to 0.5%) were pneumonia or lower respiratory tract infections, cellulitis and urinary tract infections. Fatal serious infections included pneumonia, sepsis and colitis. Rates of serious infection remained stable in patients receiving subsequent courses. In 185 rituximab-treated RA patients with active disease, subsequent treatment with a biologic DMARD, the majority of which were TNF antagonists, did not appear to increase the rate of serious infection. Thirteen serious infections were observed in 186.1 patient-years (6.99 per 100 patient-years) prior to exposure and 10 were observed in 182.3 patient-years (5.49 per 100 patient-years) after exposure.

Cardiovascular Adverse Reactions
In the pooled, placebo-controlled studies, the proportion of patients with serious cardiovascular reactions was 1.7% and 1.3% in the rituximab and placebo treatment groups, respectively. Three cardiovascular deaths occurred during the double-blind period of the RA studies including all rituximab regimens (3/769=0.4%) as compared to none in the placebo treatment group (0/389).

In the experience with rituximab in 2,578 RA patients, the rate of serious cardiac reactions was 1.93 per 100 patient-years. The rate of myocardial infarction (MI) was 0.56 per 100 patient-years (28 events in 26 patients), which is consistent with MI rates in the general RA population. These rates did not increase over three courses of rituximab.

Since patients with RA are at increased risk for cardiovascular events compared with the general population, patients with RA should be monitored throughout the infusion and RUXIENCE should be discontinued in the event of a serious or life-threatening cardiac event.

Hypophosphatemia and Hyperuricemia
In the pooled, placebo-controlled studies, newly-occurring hypophosphatemia (less than 2.0 mg/dL) was observed in 12% (67/540) of patients on rituximab versus 10% (39/398) of patients on placebo. Hypophosphatemia was more common in patients who received corticosteroids. Newly-occurring hyperuricemia (greater than 10 mg/dL) was observed in 1.5% (8/540) of patients on rituximab versus 0.3% (1/398) of patients on placebo.

In the experience with rituximab in RA patients, newly-occurring hypophosphatemia was observed in 21% (528/2570) of patients and newly-occurring hyperuricemia was observed in 2% (56/2570) of patients. The majority of the observed hypophosphatemia occurred at the time of the infusions and was transient.

Retreatment in Patients with RA
In the experience with rituximab in RA patients, 2,578 patients have been exposed to rituximab and have received up to 10 courses of rituximab in RA clinical trials, with 1,890, 1,043, and 425 patients having received at least two, three, and four courses, respectively. Most of the patients who received additional courses did so 24 weeks or more after the previous course and none were retreated sooner than 16 weeks. The rates and types of adverse reactions reported for subsequent courses of rituximab were similar to rates and types seen for a single course of rituximab.

In RA Study 2, where all patients initially received rituximab, the safety profile of patients who were retreated with rituximab was similar to those who were retreated with placebo [see Clinical Studies (14.6), Dosage and Administration (2.5)].

Granulomatosis with Polyangiitis (GPA) (Wegener's Granulomatosis) and Microscopic Polyangiitis (MPA)

Induction Treatment of Adult Patients with Active GPA/MPA (GPA/MPA Study 1)
The data presented below from GPA/MPA Study 1 (NCT00104299) reflect the experience in 197 adult patients with active GPA and MPA treated with rituximab or cyclophosphamide in a single controlled study, which was conducted in two phases: a 6-month randomized, double-blind, double-dummy, active-controlled remission induction phase and an additional 12-month remission maintenance phase [see Clinical Studies (14.7)]. In the 6-month remission induction phase, 197 patients with GPA and MPA were randomized to either rituximab 375 mg/m^2 once weekly for 4 weeks plus glucocorticoids, or oral cyclophosphamide 2 mg/kg daily (adjusted for renal function, white blood cell count, and other factors) plus glucocorticoids to induce remission. Once remission was achieved or at the end of the 6-month remission induction period, the cyclophosphamide group received azathioprine to maintain remission. The rituximab group did not receive additional therapy to maintain remission. The primary analysis was at the end of the 6-month remission induction period and the safety results for this period are described below.

Adverse reactions presented below in Table 3 were adverse events which occurred at a rate of greater than or equal to 10% in the rituximab group. This table reflects experience in 99 GPA and MPA patients treated with rituximab, with a total of 47.6 patient-years of observation and 98 GPA and MPA patients treated with cyclophosphamide, with a total of 47.0 patient-years of observation. Infection was the most common category of adverse events reported (47–62%) and is discussed below.

Table 3 Incidence of All Adverse Reactions Occurring in Greater than or Equal to 10% of Rituximab-treated Patients with Active GPA and MPA in the GPA/MPA Study 1 Up to Month 6 [The study design allowed for crossover or treatment by best medical judgment, and 13 patients in each treatment group received a second therapy during the 6-month study period.]
Adverse Reaction | Rituximab N=99 n (%) | Cyclophosphamide N=98 n (%)
Nausea | 18 (18%) | 20 (20%)
Diarrhea | 17 (17%) | 12 (12%)
Headache | 17 (17%) | 19 (19%)
Muscle Spasms | 17 (17%) | 15 (15%)
Anemia | 16 (16%) | 20 (20%)
Peripheral Edema | 16 (16%) | 6 (6%)
Insomnia | 14 (14%) | 12 (12%)
Arthralgia | 13 (13%) | 9 (9%)
Cough | 13 (13%) | 11 (11%)
Fatigue | 13 (13%) | 21 (21%)
Increased ALT | 13 (13%) | 15 (15%)
Hypertension | 12 (12%) | 5 (5%)
Epistaxis | 11 (11%) | 6 (6%)
Dyspnea | 10 (10%) | 11 (11%)
Leukopenia | 10 (10%) | 26 (27%)
Rash | 10 (10%) | 17 (17%)

Infusion-Related Reactions
Infusion-related reactions in GPA/MPA Study 1 were defined as any adverse event occurring within 24 hours of an infusion and considered to be infusion-related by investigators. Among the 99 patients treated with rituximab, 12% experienced at least one infusion-related reaction, compared with 11% of the 98 patients in the cyclophosphamide group. Infusion-related reactions included cytokine release syndrome, flushing, throat irritation, and tremor. In the rituximab group, the proportion of patients experiencing an infusion-related reaction was 12%, 5%, 4%, and 1% following the first, second, third, and fourth infusions, respectively. Patients were pre-medicated with antihistamine and acetaminophen before each rituximab infusion and were on background oral corticosteroids which may have mitigated or masked an infusion-related reaction; however, there is insufficient evidence to determine whether premedication diminishes the frequency or severity of infusion-related reactions.

Infections
In GPA/MPA Study 1, 62% (61/99) of patients in the rituximab group experienced an infection of any type compared to 47% (46/98) patients in the cyclophosphamide group by Month 6. The most common infections in the rituximab group were upper respiratory tract infections, urinary tract infections, and herpes zoster.

The incidence of serious infections was 11% in the rituximab-treated patients and 10% in the cyclophosphamide treated patients, with rates of approximately 25 and 28 per 100 patient-years, respectively. The most common serious infection was pneumonia.

Hypogammaglobulinemia
Hypogammaglobulinemia (IgA, IgG, or IgM below the lower limit of normal) has been observed in patients with GPA and MPA treated with rituximab in GPA/MPA Study 1. At 6 months, in the rituximab group, 27%, 58% and 51% of patients with normal immunoglobulin levels at baseline, had low IgA, IgG and IgM levels, respectively compared to 25%, 50%, and 46% in the cyclophosphamide group.

Follow up Treatment of Adult Patients with GPA/MPA who have Achieved Disease Control with Induction Treatment (GPA/MPA Study 2)
In GPA/MPA Study 2 (NCT00748644), an open-label, controlled, clinical study [see Clinical Studies (14.7)], evaluating the efficacy and safety of non-U.S.-licensed rituximab versus azathioprine as follow up treatment in adult patients with GPA, MPA or renal-limited ANCA-associated vasculitis who had achieved disease control after induction treatment with cyclophosphamide, a total of 57 GPA and MPA patients in disease remission received follow up treatment with two 500 mg intravenous infusions of non-U.S.-licensed rituximab, separated by two weeks on Day 1 and Day 15, followed by a 500 mg intravenous infusion every 6 months for 18 months.

The safety profile was consistent with the safety profile for rituximab in RA and GPA and MPA.

Infusion-Related Reactions
In GPA/MPA Study 2, 7/57 (12%) patients in the non-U.S.-licensed rituximab arm reported infusion-related reactions. The incidence of IRR symptoms was highest during or after the first infusion (9%) and decreased with subsequent infusions (less than 4%). One patient had two serious IRRs, two IRRs led to a dose modification, and no IRRs were severe, fatal, or led to withdrawal from the study.

Infections
In GPA/MPA Study 2, 30/57 (53%) patients in the non-U.S.-licensed rituximab arm and 33/58 (57%) in the azathioprine arm reported infections. The incidence of all grade infections was similar between the arms. The incidence of serious infections was similar in both arms (12%). The most commonly reported serious infection in the group was mild or moderate bronchitis.

Long-term, Observational Study with Rituximab in Patients with GPA/MPA (GPA/MPA Study 3)
In a long-term observational safety study (NCT01613599), 97 patients with GPA or MPA received treatment with rituximab (mean of 8 infusions [range 1–28]) for up to 4 years, according to physician standard practice and discretion. Majority of patients received doses ranging from 500 mg to 1,000 mg, approximately every 6 months. The safety profile was consistent with the safety profile for rituximab in RA and GPA and MPA.

Pemphigus Vulgaris (PV)

PV Study 1
PV Study 1 (NCT00784589), a randomized, controlled, multicenter open-label study, evaluated the efficacy and safety of non-U.S.-licensed rituximab in combination with short-term prednisone compared to prednisone monotherapy in 90 patients (74 Pemphigus Vulgaris [PV] patients and 16 Pemphigus Foliaceus [PF] patients) [see Clinical Studies (14.8)]. Safety results for the PV patient population during the 24-month treatment period are described below.

The safety profile of the non-U.S.-licensed rituximab in patients with PV was consistent with that observed in patients with rituximab-treated RA and GPA and MPA [see Adverse Reactions (6.1)].

Adverse reactions from PV Study 1 are presented below in Table 4 and were adverse events which occurred at a rate greater than or equal to 5% among PV patients treated with non-U.S.-licensed rituximab and with at least 2% absolute difference in incidence between the group treated with non-U.S.-licensed rituximab and the prednisone monotherapy group up to Month 24. No patients in the group treated with non-U.S.-licensed rituximab withdrew due to adverse reactions. The clinical study did not include sufficient number of patients to allow for direct comparison of adverse reaction rates between treatment groups.

Table 4 Incidence of All Adverse Reactions Occurring in Greater than or Equal to 5% Among PV Patients Treated with Non-U.S.-licensed Rituximab and with at Least 2% Absolute Difference in Incidence Between the Group Treated with Non-U.S.-licensed Rituximab with Short-term Prednisone and the Group Treated with Prednisone Monotherapy in PV Study 1 (Up to Month 24)
Adverse Reaction | Non-U.S.-Licensed; Rituximab + Short-term Prednisone; N=38; n (%) | Prednisone; N=36; n (%)
Infusion-related reactions [Infusion-related reactions included symptoms collected on the next scheduled visit after each infusion, and adverse reactions occurring on the day of or one day after the infusion. The most common infusion-related reactions included headaches, chills, high blood pressure, nausea, asthenia, and pain.] | 22 (58%) | N/A
Depression | 7 (18%) | 4 (11%)
Herpes simplex | 5 (13%) | 1 (3%)
Alopecia | 5 (13%) | 0 (0%)
Fatigue | 3 (8%) | 2 (6%)
Abdominal pain upper | 2 (5%) | 1 (3%)
Conjunctivitis | 2 (5%) | 0 (0%)
Dizziness | 2 (5%) | 0 (0%)
Headache | 2 (5%) | 1 (3%)
Herpes zoster | 2 (5%) | 1 (3%)
Irritability | 2 (5%) | 0 (0%)
Musculoskeletal pain | 2 (5%) | 0 (0%)
Pruritus | 2 (5%) | 0 (0%)
Pyrexia | 2 (5%) | 0 (0%)
Skin disorder | 2 (5%) | 0 (0%)
Skin papilloma | 2 (5%) | 0 (0%)
Tachycardia | 2 (5%) | 0 (0%)
Urticaria | 2 (5%) | 0 (0%)
N/A = not applicable

Infusion-Related Reactions
Infusion-related reactions were the most commonly reported adverse drug reactions (58%, 22 patients). All infusion-related reactions were mild to moderate (Grade 1 or 2) except one Grade 3 serious infusion-related reaction (arthralgia) associated with the Month 12 maintenance infusion. The proportion of patients experiencing an infusion-related reaction was 29% (11 patients), 40% (15 patients), 13% (5 patients), and 10% (4 patients) following the first, second, third, and fourth infusions, respectively. No patients were withdrawn from treatment due to infusion-related reactions. Symptoms of infusion-related reactions were similar in type and severity to those seen in RA and GPA and MPA patients [see Adverse Reactions (6.1)].

Infections
Fourteen patients (37%) in the group treated with non-U.S.-licensed rituximab experienced treatment-related infections compared to 15 patients (42%) in the prednisone group. The most common infections in the group treated with non-U.S.-licensed rituximab were herpes simplex, herpes zoster, bronchitis, urinary tract infection, fungal infection, and conjunctivitis. Three patients (8%) in the group treated with non-U.S.-licensed rituximab experienced a total of 5 serious infections (Pneumocystis jirovecii pneumonia, infective thrombosis, intervertebral discitis, lung infection, Staphylococcal sepsis) and 1 patient (3%) in the prednisone group experienced 1 serious infection (Pneumocystis jirovecii pneumonia).

PV Study 2
In PV Study 2 (NCT02383589), a randomized, double-blind, double-dummy, active-comparator, multicenter study evaluating the efficacy and safety of rituximab compared to mycophenolate mofetil (MMF) in patients with moderate to severe PV requiring oral corticosteroids, 67 PV patients received treatment with rituximab (initial 1,000 mg IV on Study Day 1 and a second 1,000 mg IV on Study Day 15 repeated at Weeks 24 and 26) for up to 52 weeks [see Clinical Studies (14.8)].

In PV Study 2, ADR defined as adverse events occurring in greater than or equal to 5% of patients in the rituximab arms and assessed as related are shown in Table 5.

Table 5 Incidence of All Adverse Reactions Occurring in Greater than or Equal to 5% of Rituximab-treated Pemphigus Vulgaris Patients (N=67) from PV Study 2 (up to Week 52)
Adverse Reactions | Rituximab; (N=67)
Infusion-related reactions | 15 (22%) [The most common infusion-related reaction symptoms/Preferred Terms for PV Study 2 in the rituximab arm were dyspnea, erythema, hyperhidrosis, flushing/hot flush, hypotension/low blood pressure, and rash/rash pruritic.]
Upper respiratory tract infection/Nasopharyngitis | 11 (16%)
Headache | 10 (15%)
Asthenia/Fatigue | 9 (13%)
Oral candidiasis | 6 (9%)
Arthralgia | 6 (9%)
Back pain | 6 (9%)
Urinary tract infection | 5 (8%)
Dizziness | 4 (6%)

Infusion-Related Reactions
In PV Study 2, IRRs occurred primarily at the first infusion and the frequency of IRRs decreased with subsequent infusions: 17.9%, 4.7%, 3.5%, and 3.5% of patients experienced IRRs at the first, second, third, and fourth infusions, respectively. In 11/15 patients who experienced at least one IRR, the IRRs were Grade 1 or 2. In 4/15 patients, Grade greater than or equal to 3 IRRs were reported and led to discontinuation of rituximab treatment; three of the four patients experienced serious [life-threatening] IRRs. Serious IRRs occurred at the first (2 patients) or second (1 patient) infusion and resolved with symptomatic treatment.

Infections
In PV Study 2, 42/67 patients (62.7%) in the rituximab arm experienced infections. The most common infections in the rituximab arm were upper respiratory tract infection, nasopharyngitis, oral candidiasis, and urinary tract infection. Six patients (9%) in the rituximab arm experienced serious infections.

Laboratory Abnormalities
In PV Study 2, in the rituximab arm, transient decreases in T-cell lymphocytes and phosphorus level were very commonly observed post-infusion. In some cases, treatment of hypophosphatemia was required.

Hypogammaglobulinemia (IgG or IgM below the lower limit of normal), including prolonged hypogammaglobulinemia (defined as Ig levels below lower limit of normal for at least 4 months) was observed in PV Study 2. Based on levels less than LLN measured at Week 16, Week 24, Week 40, and Week 52, 16.4% (11/67) of patients with normal baseline immunoglobulins had prolonged hypogammaglobulinemia (10 patients – IgM, 1 patient – both IgG and IgM) after treatment with rituximab.

6.2 Immunogenicity

The observed incidence of anti-drug antibodies is highly dependent on the sensitivity and specificity of the assay. Differences in assay methods preclude meaningful comparisons of the incidence of anti-drug antibodies in the studies described below with the incidence of anti-drug antibodies in other studies, including those of rituximab or of other rituximab products.

Using an ELISA assay, anti-rituximab antibody was detected in 4 of 356 (1.1%) patients with low-grade or follicular NHL receiving single-agent rituximab. Three of the four patients had an objective clinical response.

A total of 273/2578 (11%) patients with RA tested positive for anti-rituximab antibodies at any time after receiving rituximab. Anti-rituximab antibody positivity was not associated with increased rates of infusion-related reactions or other adverse events. Upon further treatment, the proportions of patients with infusion-related reactions were similar between anti-rituximab antibody positive and negative patients, and most reactions were mild to moderate. Four anti-rituximab antibody positive patients had serious infusion-related reactions, and the temporal relationship between anti-rituximab antibody positivity and infusion-related reaction was variable.

A total of 23/99 (23%) rituximab-treated adult patients with GPA and MPA developed anti-rituximab antibodies by 18 months in GPA/MPA Study 1. The clinical relevance of anti-rituximab antibody formation in rituximab-treated adult patients is unclear.

Using a new ELISA assay, a total of 19/34 (56%) patients with PV, who were treated with non-U.S.-licensed rituximab, tested positive for anti-rituximab antibodies by 18 months in PV Study 1. In PV Study 2, a total of 20/63 (32%) rituximab-treated PV patients tested positive for ADA by week 52 (19 patients had treatment-inducted ADA and 1 patient had treatment-enhanced ADA). The clinical relevance of anti-rituximab antibody formation in rituximab-treated PV patients is unclear.

6.3 Postmarketing Experience

The following adverse reactions have been identified during post-approval use of rituximab. Because these reactions are reported voluntarily from a population of uncertain size, it is not always possible to reliably estimate their frequency or establish a causal relationship to drug exposure.

- Hematologic: prolonged pancytopenia, marrow hypoplasia, Grade 3–4 prolonged or late-onset neutropenia, hyperviscosity syndrome in Waldenstrom's macroglobulinemia, prolonged hypogammaglobulinemia [see Warnings and Precautions (5.6)].
- Cardiac: fatal cardiac failure.
- Immune/Autoimmune Events: uveitis, optic neuritis, systemic vasculitis, pleuritis, lupus-like syndrome, serum sickness, polyarticular arthritis, and vasculitis with rash.
- Infection: viral infections, including progressive multifocal leukoencephalopathy (PML), increase in fatal infections in HIV-associated lymphoma, and a reported increased incidence of Grade 3 and 4 infections [see Warnings and Precautions (5.6)].
- Neoplasia: disease progression of Kaposi's sarcoma.
- Skin: severe mucocutaneous reactions, pyoderma gangrenosum (including genital presentation).
- Gastrointestinal: bowel obstruction and perforation.
- Pulmonary: fatal bronchiolitis obliterans and fatal interstitial lung disease.
- Nervous system: Posterior Reversible Encephalopathy Syndrome (PRES)/Reversible Posterior Leukoencephalopathy Syndrome (RPLS).

7 DRUG INTERACTIONS

Formal drug interaction studies have not been performed with rituximab products. In patients with CLL, rituximab did not alter systemic exposure to fludarabine or cyclophosphamide. In clinical trials of patients with RA, concomitant administration of methotrexate or cyclophosphamide did not alter the pharmacokinetics of rituximab.

8 USE IN SPECIFIC POPULATIONS

8.1 Pregnancy

Risk Summary

Based on human data, rituximab products can cause adverse developmental outcomes including B-cell lymphocytopenia in infants exposed in-utero (see Clinical Considerations). In animal reproduction studies, intravenous administration of rituximab to pregnant cynomolgus monkeys during the period of organogenesis caused lymphoid B-cell depletion in the newborn offspring at doses resulting in 80% of the exposure (based on AUC) of those achieved following a dose of 2 grams in humans. Advise pregnant women of the risk to a fetus.

Adverse outcomes in pregnancy occur regardless of the health of the mother or the use of medications. The background risk of major birth defects and miscarriage for the indicated populations is unknown. The estimated background risk in the U.S. general population of major birth defects is 2%–4% and of miscarriage is 15%–20% of clinically recognized pregnancies.

Clinical Considerations

Fetal/Neonatal Adverse Reactions
Observe newborns and infants for signs of infection and manage accordingly.

Data

Human Data
Postmarketing data indicate that B-cell lymphocytopenia generally lasting less than six months can occur in infants exposed to rituximab in-utero. Rituximab was detected postnatally in the serum of infants exposed in-utero.

Animal Data
An embryo-fetal developmental toxicity study was performed on pregnant cynomolgus monkeys. Pregnant animals received rituximab via the intravenous route during early gestation (organogenesis period; post coitum Days 20 through 50). Rituximab was administered as loading doses on post coitum (PC) Days 20, 21, and 22, at 15, 37.5, or 75 mg/kg/day, and then weekly on PC Days 29, 36, 43, and 50, at 20, 50, or 100 mg/kg/week. The 100 mg/kg/week dose resulted in 80% of the exposure (based on AUC) of those achieved following a dose of 2 grams in humans. Rituximab crosses the monkey placenta. Exposed offspring did not exhibit any teratogenic effects but did have decreased lymphoid tissue B cells.

A subsequent pre- and postnatal reproductive toxicity study in cynomolgus monkeys was completed to assess developmental effects including the recovery of B cells and immune function in infants exposed to rituximab in-utero. Animals were treated with a loading dose of 0, 15, or 75 mg/kg every day for 3 days, followed by weekly dosing with 0, 20, or 100 mg/kg dose. Subsets of pregnant females were treated from PC Day 20 through postpartum Day 78, PC Day 76 through PC Day 134, and from PC Day 132 through delivery and postpartum Day 28. Regardless of the timing of treatment, decreased B cells and immunosuppression were noted in the offspring of rituximab-treated pregnant animals. The B-cell counts returned to normal levels, and immunologic function was restored within 6 months postpartum.

8.2 Lactation

There are limited data on the presence of rituximab in human milk, and the effect on the breastfed child, and there are no data on the effect on milk production. Rituximab is detected in the milk of lactating cynomolgus monkeys, and maternal IgG is present in human breast milk. Rituximab has also been reported to be excreted at low concentrations in human breast milk. Given that the clinical significance of this finding for children is not known, advise women not to breastfeed during treatment with RUXIENCE and for 6 months after the last dose due to the potential of serious adverse reactions in breastfed children.

8.3 Females and Males of Reproductive Potential

Rituximab products can cause fetal harm when administered to a pregnant woman [see Use in Specific Populations (8.1)].

Pregnancy Testing

Verify pregnancy status in females of reproductive potential prior to initiating RUXIENCE.

Contraception

Females
Advise females of reproductive potential to use effective contraception during treatment with RUXIENCE and for 12 months after the last dose.

8.4 Pediatric Use

The safety and effectiveness of RUXIENCE have not been established in pediatric patients with NHL, CLL, PV or RA.

Rituximab was not studied in pediatric patients with polyarticular juvenile idiopathic arthritis (PJIA) due to concerns regarding the potential for prolonged immunosuppression as a result of B-cell depletion in the developing juvenile immune system.

8.5 Geriatric Use

Diffuse Large B-Cell NHL

Among patients with DLBCL evaluated in three randomized, active-controlled trials, 927 patients received rituximab in combination with chemotherapy. Of these, 396 (43%) were age 65 or greater and 123 (13%) were age 75 or greater. No overall differences in effectiveness were observed between these patients and younger patients. Cardiac adverse reactions, mostly supraventricular arrhythmias, occurred more frequently among elderly patients. Serious pulmonary adverse reactions were also more common among the elderly, including pneumonia and pneumonitis.

Low-Grade or Follicular Non-Hodgkin's Lymphoma

Patients with previously untreated follicular NHL evaluated in NHL Study 5 were randomized to rituximab as single-agent maintenance therapy (n=505) or observation (n=513) after achieving a response to rituximab in combination with chemotherapy. Of these, 123 (24%) patients in the rituximab arm were age 65 or older. No overall differences in safety or effectiveness were observed between these patients and younger patients. Other clinical studies of rituximab in low-grade or follicular, CD20-positive, B-cell NHL did not include sufficient numbers of patients aged 65 and over to determine whether they respond differently from younger subjects.

Chronic Lymphocytic Leukemia

Among patients with CLL evaluated in two randomized active-controlled trials, 243 of 676 rituximab-treated patients (36%) were 65 years of age or older; of these, 100 rituximab-treated patients (15%) were 70 years of age or older.

In exploratory analyses defined by age, there was no observed benefit from the addition of rituximab to fludarabine and cyclophosphamide among patients 70 years of age or older in CLL Study 1 or in CLL Study 2; there was also no observed benefit from the addition of rituximab to fludarabine and cyclophosphamide among patients 65 years of age or older in CLL Study 2 [see Clinical Studies (14.5)]. Patients 70 years or older received lower dose intensity of fludarabine and cyclophosphamide compared to younger patients, regardless of the addition of rituximab. In CLL Study 1, the dose intensity of rituximab was similar in older and younger patients, however in CLL Study 2 older patients received a lower dose intensity of rituximab.

The incidence of Grade 3 and 4 adverse reactions was higher among patients receiving R-FC who were 70 years or older compared to younger patients for neutropenia [44% vs. 31% (CLL Study 1); 56% vs. 39% (CLL Study 2)], febrile neutropenia [16% vs. 6% (NHL Study 10 (NCT00719472))], anemia [5% vs. 2% (CLL Study 1); 21% vs. 10% (CLL Study 2)], thrombocytopenia [19% vs. 8% (CLL Study 2)], pancytopenia [7% vs. 2% (CLL Study 1); 7% vs. 2% (CLL Study 2)], and infections [30% vs. 14% (CLL Study 2)].

Rheumatoid Arthritis

Among the 2,578 patients in global RA studies completed to date, 12% were 65–75 years old and 2% were 75 years old and older. The incidences of adverse reactions were similar between older and younger patients. The rates of serious adverse reactions, including serious infections, malignancies, and cardiovascular events were higher in older patients.

Granulomatosis with Polyangiitis (GPA) (Wegener's Granulomatosis) and Microscopic Polyangiitis

Of the 99 rituximab-treated GPA and MPA patients in GPA/MPA Study 1, 36 (36%) were 65 years old and over, while 8 (8%) were 75 years and over. No overall differences in efficacy were observed between patients that were 65 years old and over and younger patients. The overall incidence and rate of all serious adverse events was higher in patients 65 years old and over. The clinical study did not include sufficient numbers of patients aged 65 and over to determine whether they respond differently from younger subjects.

In GPA/MPA Study 2, 30 (26%) of the enrolled patients were at least 65 years old, of which 12 patients were exposed to non-U.S.-licensed rituximab and 18 were exposed to azathioprine. The clinical study did not include sufficient numbers of patients aged 65 and over to determine whether they respond differently from younger subjects.

Pemphigus Vulgaris

Of the 46 patients treated with non-U.S.-licensed rituximab, 15 (33%) patients were 65 years of age and older. The clinical study did not include sufficient numbers of patients aged 65 and older to determine whether they respond differently from younger patients.

11 DESCRIPTION

Rituximab-pvvr is a genetically engineered chimeric murine/human monoclonal IgG1 kappa antibody directed against the CD20 antigen. Rituximab-pvvr has an approximate molecular weight of 145 kD.

Rituximab-pvvr is produced by mammalian cell (Chinese Hamster Ovary) suspension culture in a nutrient medium.

RUXIENCE (rituximab-pvvr) injection is a sterile, preservative-free, clear to slightly opalescent, colorless to pale brownish-yellow solution for intravenous infusion. RUXIENCE is supplied at a concentration of 10 mg/mL in either 100 mg/10 mL or 500 mg/50 mL single-dose vials. Each mL of solution contains 10 mg rituximab-pvvr, 0.056 mg of edetate disodium dihydrate, 1.2 mg of L-histidine, 2.57 mg of L-histidine hydrochloride monohydrate, 0.2 mg of polysorbate 80, 85 mg of sucrose, and Water for Injection, USP. The pH is 5.8.

12 CLINICAL PHARMACOLOGY

12.1 Mechanism of Action

Rituximab-pvvr is a monoclonal antibody. Rituximab products target the CD20 antigen expressed on the surface of pre-B and mature B-lymphocytes. Upon binding to CD20, rituximab products mediate B-cell lysis. Possible mechanisms of cell lysis include complement dependent cytotoxicity (CDC) and antibody dependent cell mediated cytotoxicity (ADCC). B cells are believed to play a role in the pathogenesis of rheumatoid arthritis (RA) and associated chronic synovitis. In this setting, B cells may be acting at multiple sites in the autoimmune/inflammatory process, including through production of rheumatoid factor (RF) and other autoantibodies, antigen presentation, T-cell activation, and/or proinflammatory cytokine production.

12.2 Pharmacodynamics

Non-Hodgkin's Lymphoma (NHL)

In NHL patients, administration of rituximab resulted in depletion of circulating and tissue-based B cells. Among 166 patients in NHL Study 1 (NCT000168740), circulating CD19-positive B cells were depleted within the first three weeks with sustained depletion for up to 6 to 9 months post treatment in 83% of patients. B-cell recovery began at approximately 6 months and median B-cell levels returned to normal by 12 months following completion of treatment.

There were sustained and statistically significant reductions in both IgM and IgG serum levels observed from 5 through 11 months following rituximab administration; 14% of patients had IgM and/or IgG serum levels below the normal range.

Rheumatoid Arthritis

In RA patients, treatment with rituximab-induced depletion of peripheral B-lymphocytes, with the majority of patients demonstrating near complete depletion (CD19 counts below the lower limit of quantification, 20 cells/µL) within 2 weeks after receiving the first dose of rituximab. The majority of patients showed peripheral B-cell depletion for at least 6 months. A small proportion of patients (~4%) had prolonged peripheral B-cell depletion lasting more than 3 years after a single course of treatment.

Total serum immunoglobulin levels, IgM, IgG, and IgA were reduced at 6 months with the greatest change observed in IgM. At Week 24 of the first course of rituximab treatment, small proportions of patients experienced decreases in IgM (10%), IgG (2.8%), and IgA (0.8%) levels below the lower limit of normal (LLN). In the experience with rituximab in RA patients during repeated rituximab treatment, 23.3%, 5.5%, and 0.5% of patients experienced decreases in IgM, IgG, and IgA concentrations below LLN at any time after receiving rituximab, respectively. The clinical consequences of decreases in immunoglobulin levels in RA patients treated with rituximab are unclear.

Treatment with rituximab in patients with RA was associated with reduction of certain biologic markers of inflammation such as interleukin-6 (IL-6), C-reactive protein (CRP), serum amyloid protein (SAA), S100 A8/S100 A9 heterodimer complex (S100 A8/9), anti-citrullinated peptide (anti-CCP), and RF.

Granulomatosis with Polyangiitis (GPA) (Wegener's Granulomatosis) and Microscopic Polyangiitis

In GPA and MPA patients in GPA/MPA Study 1, peripheral blood CD19 B-cells depleted to less than 10 cells/μL following the first two infusions of rituximab, and remained at that level in most (84%) patients through Month 6. By Month 12, the majority of patients (81%) showed signs of B-cell return with counts greater than 10 cells/μL. By Month 18, most patients (87%) had counts greater than 10 cells/μL.

In GPA/MPA Study 2 where patients received non-U.S.-licensed rituximab as two 500 mg intravenous infusions separated by two weeks, followed by a 500 mg intravenous infusion at Month 6, 12, and 18, 70% (30 out of 43) of the rituximab-treated patients with CD19+ peripheral B cells evaluated post-baseline had undetectable CD19+ peripheral B cells at Month 24. At Month 24, all 37 patients with evaluable baseline CD19+ peripheral B cells and Month 24 measurements had lower CD19+ B cells relative to baseline.

12.3 Pharmacokinetics

Non-Hodgkin's Lymphoma (NHL)

Pharmacokinetics were characterized in 203 NHL patients receiving 375 mg/m^2 rituximab weekly by intravenous infusion for 4 doses. Rituximab was detectable in the serum of patients 3 to 6 months after completion of treatment.

The pharmacokinetic profile of rituximab when administered as 6 infusions of 375 mg/m^2 in combination with 6 cycles of CHOP chemotherapy was similar to that seen with rituximab alone.

Based on a population pharmacokinetic analysis of data from 298 NHL patients who received rituximab once weekly or once every three weeks, the estimated median terminal elimination half-life was 22 days (range, 6.1 to 52 days). Patients with higher CD19-positive cell counts or larger measurable tumor lesions at pretreatment had a higher clearance. However, dose adjustment for pretreatment CD19 count or size of tumor lesion is not necessary. Age and gender had no effect on the pharmacokinetics of rituximab.

Pharmacokinetics were characterized in 21 patients with CLL receiving rituximab according to the recommended dose and schedule. The estimated median terminal half-life of rituximab was 32 days (range, 14 to 62 days).

Rheumatoid Arthritis

Following administration of 2 doses of rituximab in patients with RA, the mean (±S.D.; % CV) concentrations after the first infusion (Cmax first) and second infusion (Cmax second) were 157 (±46; 29%) and 183 (±55; 30%) mcg/mL, and 318 (±86; 27%) and 381 (±98; 26%) mcg/mL for the 2 × 500 mg and 2 × 1,000 mg doses, respectively.

Based on a population pharmacokinetic analysis of data from 2,005 RA patients who received rituximab, the estimated clearance of rituximab was 0.335 L/day; volume of distribution was 3.1 L and mean terminal elimination half-life was 18.0 days (range, 5.17 to 77.5 days). Age, weight and gender had no effect on the pharmacokinetics of rituximab in RA patients.

Granulomatosis with Polyangiitis (GPA) (Wegener's Granulomatosis) and Microscopic Polyangiitis

The pharmacokinetic parameters in adult patients with GPA/MPA receiving 375 mg/m^2 intravenous rituximab or non-U.S.-licensed rituximab once weekly for four doses are summarized in Table 6.

Table 6 Population PK in Adult Patients with GPA/MPA
Parameter | Statistic | GPA/MPA Study 1
N | Number of Patients | 97
Terminal Half-life; (days) | Median; (Range) | 25; (11 to 52)
AUC0–180d; (µg/mL*day) | Median; (Range) | 10302; (3653 to 21874)
Clearance; (L/day) | Median; (Range) | 0.279; (0.113 to 0.653)
Volume of Distribution; (L) | Median; (Range) | 3.12; (2.42 to 3.91)

The population PK analysis in adults with GPA and MPA showed that male patients and patients with higher BSA or positive anti-rituximab antibody levels have higher clearance. However, further dose adjustment based on gender or anti-drug antibody status is not necessary.

Pemphigus Vulgaris

The pharmacokinetic parameters in adult PV patients receiving 1,000 mg IV infusion of rituximab at Days 1, 15, 168, and 182 are summarized in Table 7.

Table 7 Population PK in Adult PV Patients from PV Study 2
Parameter | Infusion Cycle
 | 1st cycle of 1,000 mg; Day 1 and Day 15; N=67 | 2nd cycle of 1,000 mg; Day 168 and Day 182; N=67
Terminal Half-life (days); Median; (Range) | 21.1; (9.3 to 36.2) | 26.2; (16.4 to 42.8)
Clearance (L/day); Median; (Range) | 0.30; (0.16 to 1.51) | 0.24; (0.13 to 0.45)
Central Volume of Distribution (L); Median; (Range) | 3.49; (2.48 to 5.22) | 3.49; (2.48 to 5.22)

Following the first cycle of rituximab administration, the pharmacokinetic parameters of rituximab in patients with PV were similar to those in patients with RA and in patients with GPA/MPA. Following the second cycle of rituximab administration, rituximab clearance decreased by 22% assuming Pemphigus Disease Area Index (PDAI) activity score of 0 at the start of both cycles, while the central volume of distribution remained unchanged. The presence of anti-rituximab antibodies was associated with a higher clearance resulting in lower rituximab concentrations.

Specific Populations

The clearance and volume of distribution of rituximab increased with increasing body surface area (BSA).

No formal studies were conducted to examine the effects of either renal or hepatic impairment on the pharmacokinetics of rituximab products.

Drug Interaction Studies

Formal drug interaction studies have not been performed with rituximab products.

13 NONCLINICAL TOXICOLOGY

13.1 Carcinogenesis, Mutagenesis, Impairment of Fertility

No long-term animal studies have been performed to establish the carcinogenic or mutagenic potential of rituximab products or to determine potential effects on fertility in males or females.

14 CLINICAL STUDIES

14.1 Relapsed or Refractory, Low-Grade or Follicular, CD20-Positive, B-Cell NHL

The safety and effectiveness of rituximab in relapsed, refractory CD20+ NHL were demonstrated in 3 single-arm studies enrolling 296 patients.

NHL Study 1

A multicenter, open-label, single-arm study was conducted in 166 patients with relapsed or refractory, low-grade or follicular, B-cell NHL who received 375 mg/m^2 of rituximab given as an intravenous infusion weekly for 4 doses. Patients with tumor masses greater than 10 cm or with greater than 5,000 lymphocytes/µL in the peripheral blood were excluded from the study.

Results are summarized in Table 8. The median time to onset of response was 50 days. Disease-related signs and symptoms (including B symptoms) resolved in 64% (25/39) of those patients with such symptoms at study entry.

NHL Study 2

In a multicenter, single-arm study, 37 patients with relapsed or refractory, low-grade NHL received 375 mg/m^2 of rituximab weekly for 8 doses. Results are summarized in Table 8.

NHL Study 3

In a multicenter, single-arm study, 60 patients received 375 mg/m^2 of rituximab weekly for 4 doses. All patients had relapsed or refractory, low-grade or follicular, B-cell NHL and had achieved an objective clinical response to rituximab administered 3.8–35.6 months (median 14.5 months) prior to retreatment with rituximab. Of these 60 patients, 5 received more than one additional course of rituximab. Results are summarized in Table 8.

Bulky Disease

In pooled data from studies 1 and 3, 39 patients with bulky (single lesion greater than 10 cm in diameter) and relapsed or refractory, low-grade NHL received rituximab 375 mg/m^2 weekly for 4 doses. Results are summarized in Table 8.

Table 8 Summary of Rituximab NHL Efficacy Data by Schedule and Clinical Setting
 | NHL Study 1 Weekly × 4 N=166 | NHL Study 2 Weekly × 8 N=37 | NHL Study 1 and NHL Study 3 Bulky disease, Weekly × 4 N=39 [Six of these patients are included in the first column. Thus, data from 296 intent-to-treat patients are provided in this table.] | NHL Study 3 Retreatment, Weekly × 4 N=60
Overall Response Rate | 48% | 57% | 36% | 38%
Complete Response Rate | 6% | 14% | 3% | 10%
Median Duration of Response [Kaplan-Meier projected with observed range.] , ["+" indicates an ongoing response.] , [Duration of response: interval from the onset of response to disease progression.] | 11.2 | 13.4 | 6.9 | 15.0
(Months) [Range] | [1.9 to 42.1+] | [2.5 to 36.5+] | [2.8 to 25.0+] | [3.0 to 25.1+]

14.2 Previously Untreated, Low-Grade or Follicular, CD20-Positive, B-Cell NHL

The safety and effectiveness of rituximab in previously untreated, low-grade or follicular, CD20+ NHL were demonstrated in 3 randomized, controlled trials enrolling 1,662 patients.

NHL Study 4

A total of 322 patients with previously untreated follicular NHL were randomized (1:1) to receive up to eight 3-week cycles of CVP chemotherapy alone (CVP) or in combination with rituximab 375 mg/m^2 on Day 1 of each cycle (R-CVP) in an open-label, multicenter study. The main outcome measure of the study was progression-free survival (PFS) defined as the time from randomization to the first of progression, relapse, or death.

Twenty-six percent of the study population was greater than 60 years of age, 99% had Stage III or IV disease, and 50% had an International Prognostic Index (IPI) score greater than or equal to 2. The results for PFS as determined by a blinded, independent assessment of progression are presented in Table 9. The point estimates may be influenced by the presence of informative censoring. The PFS results based on investigator assessment of progression were similar to those obtained by the independent review assessment.

Table 9 Efficacy Results in NHL Study 4
 | Study Arm
 | R-CVP N=162 |  | CVP N=160
Median PFS (years) [p <0.0001, two-sided stratified log-rank test.] | 2.4 |  | 1.4
Hazard ratio (95% CI) [Estimates of Cox regression stratified by center.] | 0.44 (0.29, 0.65)

NHL Study 5

An open-label, multicenter, randomized (1:1) study was conducted in 1,018 patients with previously untreated follicular NHL who achieved a response (CR or PR) to rituximab in combination with chemotherapy. Patients were randomized to rituximab as single-agent maintenance therapy, 375 mg/m^2 every 8 weeks for up to 12 doses or to observation. Rituximab was initiated at 8 weeks following completion of chemotherapy. The main outcome measure of the study was progression-free survival (PFS), defined as the time from randomization in the maintenance/observation phase to progression, relapse, or death, as determined by independent review.

Of the randomized patients, 40% were greater than or equal to 60 years of age, 70% had Stage IV disease, 96% had ECOG performance status (PS) 0–1, and 42% had FLIPI scores of 3–5. Prior to randomization to maintenance therapy, patients had received R-CHOP (75%), R-CVP (22%), or R-FCM (3%); 71% had a complete or unconfirmed complete response and 28% had a partial response.

PFS was longer in patients randomized to rituximab as single-agent maintenance therapy (HR: 0.54, 95% CI: 0.42, 0.70). The PFS results based on investigator assessment of progression were similar to those obtained by the independent review assessment.

Figure 1
Kaplan-Meier Plot of IRC Assessed PFS in NHL Study 5

NHL Study 6

A total of 322 patients with previously untreated low-grade, B-cell NHL who did not progress after 6 or 8 cycles of CVP chemotherapy were enrolled in an open-label, multicenter, randomized trial. Patients were randomized (1:1) to receive rituximab, 375 mg/m^2 intravenous infusion, once weekly for 4 doses every 6 months for up to 16 doses or no further therapeutic intervention. The main outcome measure of the study was progression-free survival defined as the time from randomization to progression, relapse, or death. Thirty-seven percent of the study population was greater than 60 years of age, 99% had Stage III or IV disease, and 63% had an IPI score greater than or equal to 2.

There was a reduction in the risk of progression, relapse, or death (hazard ratio estimate in the range of 0.36 to 0.49) for patients randomized to rituximab as compared to those who received no additional treatment.

14.3 Diffuse Large B-Cell NHL (DLBCL)

The safety and effectiveness of rituximab were evaluated in three randomized, active-controlled, open-label, multicenter studies with a collective enrollment of 1,854 patients. Patients with previously untreated diffuse large B-cell NHL received rituximab in combination with cyclophosphamide, doxorubicin, vincristine, and prednisone (CHOP) or other anthracycline-based chemotherapy regimens.

NHL Study 7

A total of 632 patients age greater than or equal to 60 years with DLBCL (including primary mediastinal B‑cell lymphoma) were randomized in a 1:1 ratio to treatment with CHOP or R-CHOP. Patients received 6 or 8 cycles of CHOP, each cycle lasting 21 days. All patients in the R-CHOP arm received 4 doses of rituximab 375 mg/m^2 on Days –7 and –3 (prior to Cycle 1) and 48–72 hours prior to Cycles 3 and 5. Patients who received 8 cycles of CHOP also received rituximab prior to Cycle 7. The main outcome measure of the study was progression‑free survival, defined as the time from randomization to the first of progression, relapse, or death. Responding patients underwent a second randomization to receive rituximab or no further therapy.

Among all enrolled patients, 62% had centrally confirmed DLBCL histology, 73% had Stage III–IV disease, 56% had IPI scores greater than or equal to 2, 86% had ECOG performance status of less than 2, 57% had elevated LDH levels, and 30% had two or more extranodal disease sites involved. Efficacy results are presented in Table 10. These results reflect a statistical approach which allows for an evaluation of rituximab administered in the induction setting that excludes any potential impact of rituximab given after the second randomization.

Analysis of results after the second randomization in NHL Study 7 demonstrates that for patients randomized to R-CHOP, additional rituximab exposure beyond induction was not associated with further improvements in progression-free survival or overall survival.

NHL Study 8

A total of 399 patients with DLBCL, age greater than or equal to 60 years, were randomized in a 1:1 ratio to receive CHOP or R-CHOP. All patients received up to eight 3-week cycles of CHOP induction; patients in the R-CHOP arm received rituximab 375 mg/m^2 on Day 1 of each cycle. The main outcome measure of the study was event-free survival, defined as the time from randomization to relapse, progression, change in therapy, or death from any cause. Among all enrolled patients, 80% had Stage III or IV disease, 60% of patients had an age-adjusted IPI greater than or equal to 2, 80% had ECOG performance status scores less than 2, 66% had elevated LDH levels, and 52% had extranodal involvement in at least two sites. Efficacy results are presented in Table 10.

NHL Study 9

A total of 823 patients with DLBCL, aged 18–60 years, were randomized in a 1:1 ratio to receive an anthracycline-containing chemotherapy regimen alone or in combination with rituximab. The main outcome measure of the study was time to treatment failure, defined as time from randomization to the earliest of progressive disease, failure to achieve a complete response, relapse, or death. Among all enrolled patients, 28% had Stage III–IV disease, 100% had IPI scores of less than or equal to 1, 99% had ECOG performance status of less than 2, 29% had elevated LDH levels, 49% had bulky disease, and 34% had extranodal involvement. Efficacy results are presented in Table 10.

Table 10 Efficacy Results in NHL Studies 7, 8, and 9
 | NHL Study 7; (n=632) |  | NHL Study 8; (n=399) |  | NHL Study 9; (n=823)
 | R-CHOP | CHOP | R-CHOP | CHOP | R-Chemo | Chemo
Main outcome | Progression-free survival; (years) |  | Event-free survival; (years) |  | Time to treatment failure; (years)
Median of main outcome measure | 3.1 | 1.6 | 2.9 | 1.1 | NE [NE=Not reliably estimable.] | NE
Hazard ratio [R-CHOP vs. CHOP.] | 0.69 [Significant at p <0.05, 2-sided.] |  | 0.60 |  | 0.45
Overall survival at 2 years [Kaplan-Meier estimates.] | 74% | 63% | 69% | 58% | 95% | 86%
Hazard ratio | 0.72 |  | 0.68 |  | 0.40

In NHL Study 8, overall survival estimates at 5 years were 58% vs. 46% for R-CHOP and CHOP, respectively.

14.4 Ninety-Minute Infusions in Previously Untreated Follicular NHL and DLBCL

In NHL Study 10, a total of 363 patients with previously untreated follicular NHL (n=113) or DLBCL (n=250) were evaluated in a prospective, open-label, multicenter, single-arm trial for the safety of 90-minute rituximab infusions. Patients with follicular NHL received rituximab 375 mg/m^2 plus CVP chemotherapy. Patients with DLBCL received rituximab 375 mg/m^2 plus CHOP chemotherapy. Patients with clinically significant cardiovascular disease were excluded from the study. Patients were eligible for a 90-minute infusion at Cycle 2 if they did not experience a Grade 3–4 infusion-related adverse event with Cycle 1 and had a circulating lymphocyte count less than or equal to 5,000/mm^3 before Cycle 2. All patients were pre-medicated with acetaminophen and an antihistamine and received the glucocorticoid component of their chemotherapy prior to rituximab infusion. The main outcome measure was the development of Grade 3–4 infusion-related reactions on the day of, or day after, the 90-minute infusion at Cycle 2 [see Adverse Reactions (6.1)].

Eligible patients received their Cycle 2 rituximab infusion over 90 minutes as follows: 20% of the total dose given in the first 30 minutes and the remaining 80% of the total dose given over the next 60 minutes [see Dosage and Administration (2.1)]. Patients who tolerated the 90-minute rituximab infusion at Cycle 2 continued to receive subsequent rituximab infusions at the 90-minute infusion rate for the remainder of the treatment regimen (through Cycle 6 or Cycle 8).

The incidence of Grade 3–4 infusion-related reactions at Cycle 2 was 1.1% (95% CI [0.3%, 2.8%]) among all patients, 3.5% (95% CI [1.0%, 8.8%]) for those patients treated with R-CVP, and 0.0% (95% CI [0.0%, 1.5%]) for those patients treated with R-CHOP. For Cycles 2–8, the incidence of Grade 3–4 infusion-related reactions was 2.8% (95% CI [1.3%, 5.0%]). No acute fatal infusion-related reactions were observed.

14.5 Chronic Lymphocytic Leukemia (CLL)

The safety and effectiveness of rituximab were evaluated in two randomized (1:1) multicenter open-label studies comparing FC alone or in combination with rituximab for up to 6 cycles in patients with previously untreated CLL [CLL Study 1 (n=817)] or previously treated CLL [CLL Study 2 (n=552)]. Patients received fludarabine 25 mg/m^2/day and cyclophosphamide 250 mg/m^2/day on days 1, 2, and 3 of each cycle, with or without rituximab. In both studies, seventy-one percent of CLL patients received 6 cycles and 90% received at least 3 cycles of rituximab-based therapy.

In CLL Study 1, 30% of patients were 65 years or older, 31% were Binet stage C, 45% had B symptoms, more than 99% had ECOG performance status (PS) 0–1, 74% were male, and 100% were White. In CLL Study 2, 44% of patients were 65 years or older, 28% had B symptoms, 82% received a prior alkylating drug, 18% received prior fludarabine, 100% had ECOG PS 0–1, 67% were male, and 98% were White.

The main outcome measure in both studies was progression-free survival (PFS), defined as the time from randomization to progression, relapse, or death, as determined by investigators (CLL Study 1) or an independent review committee (CLL Study 2). The investigator assessed results in CLL Study 2 were supportive of those obtained by the independent review committee. Efficacy results are presented in Table 11.

Table 11 Efficacy Results in CLL Studies 1 and 2
 | CLL Study 1 [As defined in 1996 National Cancer Institute Working Group guidelines.]; (Previously untreated) |  | CLL Study 2; (Previously treated)
 | R-FC; N=408 | FC; N=409 | R-FC; N=276 | FC; N=276
Median PFS (months) | 39.8 | 31.5 | 26.7 | 21.7
Hazard ratio (95% CI) | 0.56 (0.43, 0.71) |  | 0.76 (0.6, 0.96)
P value (Log-Rank test) | <0.01 |  | 0.02
Response rate | 86% | 73% | 54% | 45%
(95% CI) | (82, 89) | (68, 77) | (48, 60) | (37, 51)

Across both studies, 243 of 676 rituximab-treated patients (36%) were 65 years of age or older and 100 rituximab-treated patients (15%) were 70 years of age or older. The results of exploratory subset analyses in elderly patients are presented in Table 12.

Table 12 Efficacy Results in CLL Studies 1 and 2 in Subgroups Defined by Age [From exploratory analyses.]
Age subgroup | CLL Study 1 |  | CLL Study 2
Age subgroup | Number of; Patients | Hazard Ratio for; PFS (95% CI) | Number of; Patients | Hazard Ratio for; PFS (95% CI)
Age less than 65 yrs | 572 | 0.52 (0.39, 0.70) | 313 | 0.61 (0.45, 0.84)
Age greater than or equal to 65 yrs | 245 | 0.62 (0.39, 0.99) | 233 | 0.99 (0.70, 1.40)
Age less than 70 yrs | 736 | 0.51 (0.39, 0.67) | 438 | 0.67 (0.51, 0.87)
Age greater than or equal to 70 yrs | 81 | 1.17 (0.51, 2.66) | 108 | 1.22 (0.73, 2.04)

14.6 Rheumatoid Arthritis (RA)

Reducing the Signs and Symptoms: Initial and Retreatment Courses

The efficacy and safety of rituximab were evaluated in two randomized, double-blind, placebo-controlled studies of adult patients with moderately-to-severely-active RA who had a prior inadequate response to at least one TNF inhibitor. Patients were 18 years of age or older, diagnosed with active RA according to American College of Rheumatology (ACR) criteria, and had at least 8 swollen and 8 tender joints.

In RA Study 1 (NCT00468546), patients were randomized to receive either rituximab 2 × 1,000 mg + MTX or placebo + MTX for 24 weeks. Further courses of rituximab 2 × 1,000 mg + MTX were administered in an open‑label extension study at a frequency determined by clinical evaluation, but no sooner than 16 weeks after the preceding course of rituximab. In addition to the intravenous premedication, glucocorticoids were administered orally on a tapering schedule from baseline through Day 14. The proportions of patients achieving ACR 20, 50, and 70 responses at Week 24 of the placebo-controlled period are shown in Table 13.

In RA Study 2 (NCT00266227), all patients received the first course of rituximab 2 × 1,000 mg + MTX. Patients who experienced ongoing disease activity were randomized to receive a second course of either rituximab 2 × 1,000 mg + MTX or placebo + MTX, the majority between Weeks 24–28. The proportions of patients achieving ACR 20, 50, and 70 responses at Week 24, before the retreatment course, and at Week 48, after retreatment, are shown in Table 13.

Table 13 ACR Responses in RA Study 1 and RA Study 2 (Percent of Patients) (Modified Intent-to-Treat Population)
Inadequate Response to TNF Antagonists
RA Study 1 24 Week Placebo-Controlled (Week 24) |  |  |  |  | RA Study 2 Placebo-Controlled Retreatment (Week 24 and Week 48)
Response | Placebo + MTX n=201 | Rituximab + MTX n=298 | Treatment Difference (Rituximab – Placebo) (95% CI) |  | Response | Placebo + MTX Retreatment n=157 | Rituximab; +; MTX Retreatment n=318 | Treatment Difference (Rituximab – Placebo) [In RA Study 2, all patients received a first course of rituximab 2 × 1,000 mg. Patients who experienced ongoing disease activity were randomized to receive a second course of either rituximab 2 × 1,000 mg + MTX or Placebo + MTX at or after Week 24.] , [Since all patients received a first course of rituximab, no comparison between Placebo + MTX and rituximab + MTX is made at Week 24.] , [For RA Study 1, weighted difference stratified by region (US, rest of the world) and Rheumatoid Factor (RF) status (positive greater than 20 IU/mL, negative less than 20 IU/mL) at baseline; For RA Study 2, weighted difference stratified by RF status at baseline and greater than or equal to 20% improvement from baseline in both SJC and TJC at Week 24 (Yes/No).] (95% CI)
ACR20 |  |  |  |  | ACR20
Week 24 | 18% | 51% | 33% (26%, 41%) |  | Week 24 | 48% | 45% | NA
 |  |  |  |  | Week 48 | 45% | 54% | 11% (2%, 20%)
ACR50 |  |  |  |  | ACR50
Week 24 | 5% | 27% | 21% (15%, 27%) |  | Week 24 | 27% | 21% | NA
 |  |  |  |  | Week 48 | 26% | 29% | 4% (-4%, 13%)
ACR70 |  |  |  |  | ACR70
Week 24 | 1% | 12% | 11% (7%, 15%) |  | Week 24 | 11% | 8% | NA
 |  |  |  |  | Week 48 | 13% | 14% | 1% (-5%, 8%)

Improvement was also noted for all components of ACR response following treatment with rituximab, as shown in Table 14.

Table 14 Components of ACR Response at Week 24 in RA Study 1 (Modified Intent-to-Treat Population)
Inadequate Response to TNF Antagonists
 | Placebo + MTX (n=201) |  | Rituximab + MTX (n=298)
Parameter (median) | Baseline | Wk 24 | Baseline | Wk 24
Tender Joint Count | 31.0 | 27.0 | 33.0 | 13.0
Swollen Joint Count | 20.0 | 19.0 | 21.0 | 9.5
Physician Global Assessment [Visual Analog Scale: 0=best, 100=worst.] | 71.0 | 69.0 | 71.0 | 36.0
Patient Global Assessment | 73.0 | 68.0 | 71.0 | 41.0
Pain | 68.0 | 68.0 | 67.0 | 38.5
Disability Index (HAQ) [Disability Index of the Health Assessment Questionnaire: 0=best, 3=worst.] | 2.0 | 1.9 | 1.9 | 1.5
CRP (mg/dL) | 2.4 | 2.5 | 2.6 | 0.9

The time course of ACR 20 response for RA Study 1 is shown in Figure 2. Although both treatment groups received a brief course of intravenous and oral glucocorticoids, resulting in similar benefits at Week 4, higher ACR 20 responses were observed for the rituximab group by Week 8. A similar proportion of patients achieved these responses through Week 24 after a single course of treatment (2 infusions) with rituximab. Similar patterns were demonstrated for ACR 50 and 70 responses.

Figure 2
Percent of Patients Achieving ACR 20 Response by Visit [The same patients may not have responded at each time point.]
RA Study 1 (Inadequate Response to TNF Antagonists)

Radiographic Response

In RA Study 1, structural joint damage was assessed radiographically and expressed as changes in Genant-modified Total Sharp Score (TSS) and its components, the erosion score (ES) and the joint space narrowing (JSN) score. Rituximab + MTX slowed the progression of structural damage compared to placebo + MTX after 1 year as shown in Table 15.

Table 15 Mean Radiographic Change from Baseline to 104 Weeks in RA Study 1
Inadequate Response to TNF Antagonists
Parameter | Rituximab; 2 × 1,000 mg + MTX [Patients received up to 2 years of treatment with rituximab + MTX.] | Placebo + MTX [Patients receiving Placebo + MTX. Patients receiving Placebo + MTX could have received retreatment with rituximab + MTX from Week 16 onward.] | Treatment Difference (Placebo – Rituximab) | 95% CI
Change during First Year
TSS | 0.66 | 1.77 | 1.11 | (0.47, 1.75)
ES | 0.44 | 1.19 | 0.75 | (0.32, 1.19)
JSN Score | 0.22 | 0.58 | 0.36 | (0.10, 0.62)
Change during Second Year [Based on radiographic scoring following 104 weeks of observation.]
TSS | 0.48 | 1.04 | — | —
ES | 0.28 | 0.62 | — | —
JSN Score | 0.20 | 0.42 | — | —

In RA Study 1 and its open-label extension, 70% of patients initially randomized to rituximab + MTX and 72% of patients initially randomized to placebo + MTX were evaluated radiographically at Year 2. As shown in Table 15, progression of structural damage in rituximab + MTX patients was further reduced in the second year of treatment.

Following 2 years of treatment with rituximab + MTX, 57% of patients had no progression of structural damage. During the first year, 60% of rituximab + MTX treated patients had no progression, defined as a change in TSS of zero or less compared to baseline, compared to 46% of placebo + MTX treated patients. In their second year of treatment with rituximab + MTX, more patients had no progression than in the first year (68% vs. 60%), and 87% of the rituximab + MTX treated patients who had no progression in the first year also had no progression in the second year.

Lesser Efficacy of 500 vs. 1,000 mg Treatment Courses for Radiographic Outcomes

RA Study 3 (NCT00299104) is a randomized, double-blind, placebo-controlled study which evaluated the effect of placebo + MTX compared to rituximab 2 × 500 mg + MTX and rituximab 2 × 1,000 mg + MTX treatment courses in MTX-naïve RA patients with moderately-to-severely-active disease. Patients received a first course of two infusions of rituximab or placebo on Days 1 and 15. MTX was initiated at 7.5 mg/week and escalated up to 20 mg/week by Week 8 in all three treatment arms. After a minimum of 24 weeks, patients with ongoing disease activity were eligible to receive retreatment with additional courses of their assigned treatment. After one year of treatment, the proportion of patients achieving ACR 20/50/70 responses were similar in both rituximab dose groups and were higher than in the placebo group. However, with respect to radiographic scores, only the rituximab 1,000 mg treatment group demonstrated a statistically significant reduction in TSS: a change of 0.36 units compared to 1.08 units for the placebo group, a 67% reduction.

Physical Function Response

RA Study 4 (NCT00299130) is a randomized, double-blind, placebo-controlled study in adult RA patients with moderately-to-severely-active disease with inadequate response to MTX. Patients were randomized to receive an initial course of rituximab 500 mg, rituximab 1,000 mg, or placebo in addition to background MTX.

Physical function was assessed at Weeks 24 and 48 using the Health Assessment Questionnaire Disability Index (HAQ-DI). From baseline to Week 24, a greater proportion of rituximab-treated patients had an improvement in HAQ-DI of at least 0.22 (a minimal clinically important difference) and a greater mean HAQ-DI improvement compared to placebo, as shown in Table 16. HAQ-DI results for the rituximab 500 mg treatment group were similar to the rituximab 1,000 mg treatment group; however radiographic responses were not assessed (see Dosing Precaution in the Radiographic Responses section above). These improvements were maintained at 48 weeks.

Table 16 Improvement from Baseline in Health Assessment Questionnaire Disability Index (HAQ-DI) at Week 24 in RA Study 4
 | Placebo + MTX n=172 | Rituximab 2 × 1,000 mg + MTX n=170 | Treatment Difference (Rituximab - Placebo) [Adjusted difference stratified by region (US, rest of the world) and Rheumatoid Factor (RF) status (positive greater than or equal to 20 IU/mL, negative less than 20 IU/mL) at baseline.] (95% CI)
Mean Improvement from Baseline | 0.19 | 0.42 | 0.23 (0.11, 0.34)
Percent of patients with "Improved" score (Change from Baseline greater than or equal to MCID) [Minimal Clinically Important Difference: MCID for HAQ=0.22.] | 48% | 58% | 11% (0%, 21%)

14.7 Granulomatosis with Polyangiitis (GPA) (Wegener's Granulomatosis) and Microscopic Polyangiitis (MPA)

Induction Treatment of Adult Patients with Active Disease (GPA/MPA Study 1)

A total of 197 patients with active, severe GPA and MPA (two forms of ANCA‑Associated Vasculitides) were treated in a randomized, double-blind, active-controlled multicenter, non-inferiority study, conducted in two phases – a 6-month remission induction phase and a 12-month remission maintenance phase. Patients were 15 years of age or older, diagnosed with GPA (75% of patients) or MPA (24% of patients) according to the Chapel Hill Consensus conference criteria (1% of the patients had unknown vasculitis type). All patients had active disease, with a Birmingham Vasculitis Activity Score for Granulomatosis with Polyangiitis (BVAS/GPA) greater than or equal to 3, and their disease was severe, with at least one major item on the BVAS/GPA. Ninety-six (49%) of patients had new disease and 101 (51%) of patients had relapsing disease.

Patients in both arms received 1,000 mg of pulse intravenous methylprednisolone per day for 1 to 3 days within 14 days prior to initial infusion. Patients were randomized in a 1:1 ratio to receive either rituximab 375 mg/m^2 once weekly for 4 weeks or oral cyclophosphamide 2 mg/kg daily for 3 to 6 months in the remission induction phase. Patients were pre-medicated with antihistamine and acetaminophen prior to rituximab infusion. Following intravenous corticosteroid administration, all patients received oral prednisone (1 mg/kg/day, not exceeding 80 mg/day) with pre-specified tapering. Once remission was achieved or at the end of the 6-month remission induction period, the cyclophosphamide group received azathioprine to maintain remission. The rituximab group did not receive additional therapy to maintain remission. The main outcome measure for both GPA and MPA patients was achievement of complete remission at 6 months defined as a BVAS/GPA of 0, and off glucocorticoid therapy. The pre-specified non-inferiority margin was a treatment difference of 20%. As shown in Table 17, the study demonstrated non-inferiority of rituximab to cyclophosphamide for complete remission at 6 months.

Table 17 Percentage of Patients with GPA/MPA Who Achieved Complete Remission at 6 Months (Intent-to-Treat Population)
 | Rituximab (n=99) | Cyclophosphamide (n=98) | Treatment Difference (Rituximab – Cyclophosphamide)
Rate | 64% | 53% | 11%
95.1% [The 95.1% confidence level reflects an additional 0.001 alpha to account for an interim efficacy analysis.] CI | (54%, 73%) | (43%, 63%) | (-3%, 24%) [Non-inferiority was demonstrated because the lower bound was higher than the prespecified non-inferiority margin (-3% greater than -20%).]

Complete Remission (CR) at 12 and 18 Months
In the rituximab group, 44% of patients achieved CR at 6 and 12 months, and 38% of patients achieved CR at 6, 12, and 18 months. In patients treated with cyclophosphamide (followed by azathioprine for maintenance of CR), 38% of patients achieved CR at 6 and 12 months, and 31% of patients achieved CR at 6, 12, and 18 months.

Retreatment of Flares with Rituximab
Based upon investigator judgment, 15 patients received a second course of rituximab therapy for treatment of relapse of disease activity which occurred between 8 and 17 months after the induction treatment course of rituximab.

Follow up Treatment of Adult Patients with GPA/MPA who have achieved disease control with other Immunosuppressant (GPA/MPA Study 2)

A total of 115 patients (86 with GPA, 24 with MPA, and 5 with renal-limited ANCA-associated vasculitis) in disease remission were randomized to receive azathioprine (58 patients) or non-U.S.-licensed rituximab (57 patients) in this open-label, prospective, multicenter, randomized, active-controlled study. Eligible patients were 21 years and older and had either newly diagnosed (80%) or relapsing disease (20%). A majority of the patients were ANCA-positive. Remission of active disease was achieved using a combination of glucocorticoids and cyclophosphamide. Within a maximum of 1 month after the last cyclophosphamide dose, eligible patients (based on BVAS of 0), were randomized in a 1:1 ratio to receive either non-U.S.-licensed rituximab or azathioprine.

The non-U.S.-licensed rituximab was administered as two 500 mg intravenous infusions separated by two weeks (on Day 1 and Day 15) followed by a 500 mg intravenous infusion every 6 months for 18 months. Azathioprine was administered orally at a dose of 2 mg/kg/day for 12 months, then 1.5 mg/kg/day for 6 months, and finally 1 mg/kg/day for 4 months; treatment was discontinued after 22 months. Prednisone treatment was tapered and then kept at a low dose (approximately 5 mg per day) for at least 18 months after randomization. Prednisone dose tapering and the decision to stop prednisone treatment after Month 18 were left at the investigator's discretion.

Planned follow-up was until Month 28 (10 or 6 months, respectively, after the last non-U.S.-licensed rituximab infusion or azathioprine dose). The primary endpoint was the occurrence of major relapse (defined by the reappearance of clinical and/or laboratory signs of vasculitis activity that could lead to organ failure or damage, or could be life-threatening) through Month 28.

By Month 28, major relapse occurred in 3 patients (5%) in the non-U.S.-licensed rituximab group and 17 patients (29%) in the azathioprine group.

The observed cumulative incidence rate of first major relapse during the 28 months was lower in patients on non-U.S.-licensed rituximab relative to azathioprine (Figure 3).

Figure 3
Cumulative Incidence Over Time of First Major Relapse in Patients with GPA/MPA

Patients were censored at the last follow up dates if they had no event.

14.8 Pemphigus Vulgaris (PV)

PV Study 1 (NCT00784589)

Non-U.S.-licensed rituximab in combination with short-term prednisone was compared to prednisone monotherapy as first-line treatment in 90 newly diagnosed adult patients with moderate to severe pemphigus (74 Pemphigus Vulgaris [PV] and 16 Pemphigus Foliaceus [PF]) in this randomized, open-label, controlled, multicenter study (PV Study 1). Patients were between 19 and 79 years of age and had not received prior therapies for pemphigus. In the PV population, 5 (13%) patients in the group treated with non-U.S.-licensed rituximab and 3 (8%) patients in the prednisone group had moderate disease and 33 (87%) patients in the group treated with non-U.S.-licensed rituximab and 33 (92%) patients in the prednisone group had severe disease according to disease severity defined by Harman’s criteria.

Patients were stratified by baseline disease severity (moderate or severe) and randomized 1:1 to receive either the non-U.S.-licensed rituximab and short-term prednisone or long-term prednisone monotherapy. Patients were pre-medicated with antihistamine, acetaminophen and methylprednisolone prior to infusion of the non-U.S.-licensed rituximab. Patients randomized to the group treated with non-U.S.-licensed rituximab received an initial intravenous infusion of 1,000 mg non-U.S.-licensed rituximab on Study Day 1 in combination with a short-term regimen of 0.5 mg/kg/day oral prednisone tapered off over 3 months if they had moderate disease or 1 mg/kg/day oral prednisone tapered off over 6 months if they had severe disease. All patients received a second intravenous infusion of 1,000 mg non-U.S.-licensed rituximab on Study Day 15. Maintenance infusions of 500 mg non-U.S.-licensed rituximab were administered at Months 12 and 18. Patients randomized to the prednisone monotherapy group received an initial 1 mg/kg/day oral prednisone tapered off over 12 months if they had moderate disease or 1.5 mg/kg/day oral prednisone tapered off over 18 months if they had severe disease. Patients in the group treated with non-U.S.-licensed rituximab who relapsed could receive an additional infusion of 1,000 mg non-U.S.-licensed rituximab in combination with reintroduced or escalated prednisone dose. Maintenance and relapse infusions were administered no sooner than 16 weeks following the previous infusion.

The primary endpoint for the study was complete remission (complete epithelialization and absence of new and/or established lesions) at Month 24 without the use of prednisone therapy for 2 months or more (CRoff for greater than or equal to 2 months).

The results of the trial are presented in Table 18.

Table 18 Percentage of Pemphigus Patients in Complete Remission Off Corticosteroid Therapy for Two Months or More (CRoff greater than or equal to 2 months) at Month 24, PV Study 1 (Intent-to-Treat Population)
 | Non-U.S.-Licensed Rituximab +; Short-term Prednisone; N=46 | Prednisone; N=44
Number of responders; (response rate [%]) | 41 (89%) | 15 (34%)
PV patients | 34/38 (90%) | 10/36 (28%)
PF patients | 7/8 (88%) | 5/8 (63%)

PV Study 2 (NCT02383589)

In a randomized, double-blind, double-dummy, active-comparator, multicenter study, the efficacy and safety of rituximab compared to mycophenolate mofetil (MMF) were evaluated in patients with moderate to severe PV receiving 60-120 mg/day oral prednisone or equivalent (1.0-1.5 mg/kg/day) at study entry and tapered to reach a dose of 60 or 80 mg/day by Day 1. Patients had a confirmed diagnosis of PV within the previous 24 months and evidence of moderate to severe disease defined as a total Pemphigus Disease Area Index (PDAI) activity score of greater than or equal to 15. The study consisted of a screening period of up to 28 days, a 52-week double-blind treatment period, and a 48-week safety follow up period.

One hundred and thirty-five patients were randomized to treatment with rituximab 1,000 mg administered on Day 1, Day 15, Week 24 and Week 26 or oral MMF 2 g/day (starting at 1 g/day on Day 1 and titrated to achieve a goal of 2 g/day by Week 2) for 52 weeks in combination with an initial dose of 60 or 80 mg oral prednisone with the aim of tapering to 0 mg/day by Week 24. Randomization was stratified by duration of PV (within the 1 year prior to screening or greater than 1 year) and geographical region. A dual-assessor approach was used during the study for efficacy and safety evaluations to prevent potential unblinding.

One hundred and twenty-five patients (excluding exploratory data from ten telemedicine patients) were analyzed for efficacy (Modified Intent-to-Treat Population). The primary efficacy endpoint for this study was the proportion of subjects achieving sustained complete remission defined as achieving healing of lesions with no new active lesions (i.e., PDAI activity score of 0) while on 0 mg/day prednisone or equivalent, and maintaining this response for at least 16 consecutive weeks, during the 52-week treatment period.

Secondary endpoints included cumulative oral corticosteroid dose and the total number of disease flares.

The results of the trial are presented in Table 19.

Table 19 Percentage of PV Patients Who Achieved Sustained Complete Remission Off Corticosteroid Therapy for 16 Weeks or More at Week 52 (Modified Intent-to-Treat Population)
 | Rituximab; (N=62) | MMF; (N=63) | Difference (95% CI)
Number of responders (response rate [%]) | 25 (40.3%) | 6 (9.5%) | 30.80% (14.70%, 45.15%)
MMF = Mycophenolate mofetil. CI = Confidence Interval.

Glucocorticoid Exposure
The median (min, max) cumulative oral prednisone dose at Week 52 was 2,775 mg (450; 22,180) in the rituximab group compared to 4,005 mg (900; 19,920) in the MMF group. Topical corticosteroid use and pre-infusion IV methylprednisolone were not included in this analysis. Prior to each infusion, the rituximab group received IV methylprednisolone 100 mg and the MMF group received IV saline solution.

Disease Flare
Disease flare was defined as an appearance of 3 or more new lesions a month that do not heal spontaneously within 1 week or by the extension of established lesions in a patient who has achieved disease control. The total number of disease flares was lower in patients treated with rituximab compared to MMF (6 vs. 44).

16 HOW SUPPLIED/STORAGE AND HANDLING

RUXIENCE (rituximab-pvvr) injection is a sterile, preservative-free, clear to slightly opalescent, colorless to pale brownish-yellow solution for intravenous infusion supplied as follows:

Carton contents | NDC number
One 100 mg/10 mL (10 mg/mL) single-dose vial | NDC 0069-0238-01
One 500 mg/50 mL (10 mg/mL) single-dose vial | NDC 0069-0249-01

STORAGE AND HANDLING

Store RUXIENCE vials refrigerated at 2°C to 8°C (36°F to 46°F) in the original carton. RUXIENCE vials should be protected from direct sunlight. Do not freeze or shake.

17 PATIENT COUNSELING INFORMATION

Advise the patient to read the FDA-approved patient labeling (Medication Guide).

Infusion-Related Reactions

Inform patients about the signs and symptoms of infusion-related reactions. Advise patients to contact their healthcare provider immediately to report symptoms of infusion-related reactions including urticaria, hypotension, angioedema, sudden cough, breathing problems, weakness, dizziness, palpitations, or chest pain [see Warnings and Precautions (5.1)].

Severe Mucocutaneous Reactions

Advise patients to contact their healthcare provider immediately for symptoms of severe mucocutaneous reactions, including painful sores or ulcers on the mouth, blisters, peeling skin, rash, and pustules [see Warnings and Precautions (5.2)].

Hepatitis B Virus Reactivation

Advise patients to contact their healthcare provider immediately for symptoms of hepatitis including worsening fatigue or yellow discoloration of skin or eyes [see Warnings and Precautions (5.3)].

Progressive Multifocal Leukoencephalopathy (PML)

Advise patients to contact their healthcare provider immediately for signs and symptoms of PML, including new or changes in neurological symptoms such as confusion, dizziness or loss of balance, difficulty talking or walking, decreased strength or weakness on one side of the body, or vision problems [see Warnings and Precautions (5.4)].

Tumor Lysis Syndrome (TLS)

Advise patients to contact their healthcare provider immediately for signs and symptoms of tumor lysis syndrome such as nausea, vomiting, diarrhea, and lethargy [see Warnings and Precautions (5.5)].

Infections

Advise patients to contact their healthcare provider immediately for signs and symptoms of infections including fever, cold symptoms (e.g., rhinorrhea or laryngitis), flu symptoms (e.g., cough, fatigue, body aches), earache or headache, dysuria, oral herpes simplex infection, and painful wounds with erythema and advise patients of the increased risk of infections during and after treatment with RUXIENCE [see Warnings and Precautions (5.6)].

Cardiovascular Adverse Reactions

Advise patients of the risk of cardiovascular adverse reactions, including ventricular fibrillation, myocardial infarction, and cardiogenic shock. Advise patients to contact their healthcare provider immediately to report chest pain and irregular heartbeats [see Warnings and Precautions (5.7)].

Renal Toxicity

Advise patients of the risk of renal toxicity. Inform patients of the need for healthcare providers to monitor kidney function [see Warnings and Precautions (5.8)].

Bowel Obstruction and Perforation

Advise patients to contact their healthcare provider immediately for signs and symptoms of bowel obstruction and perforation, including severe abdominal pain or repeated vomiting [see Warnings and Precautions (5.9)].

Embryo-Fetal Toxicity

Advise pregnant women of the potential risk to a fetus. Advise females of reproductive potential to inform their healthcare provider of a known or suspected pregnancy [see Warnings and Precautions (5.11), Use in Specific Populations (8.1)].

Advise females of reproductive potential to use effective contraception during treatment with RUXIENCE and for 12 months after the last dose [see Use in Specific Populations (8.3)].

Lactation

Advise women not to breastfeed during treatment with RUXIENCE and for 6 months after the last dose [see Use in Specific Populations (8.2)].

Manufactured by
Pfizer Ireland Pharmaceuticals
Cork, Ireland, P43 X336
U.S. License No. 2060

Distributed by
Pfizer Labs
Division of Pfizer Inc. New York, NY 10001

This product’s labeling may have been updated. For the most recent prescribing information, please visit www.pfizer.com.

LAB-1273-6.0

MEDICATION GUIDE
RUXIENCE® (RUKSee-ents)
(rituximab-pvvr)
injection

What is the most important information I should know about RUXIENCE?
RUXIENCE can cause serious side effects that can lead to death, including:

- Infusion-related reactions. Infusion-related reactions are very common side effects of RUXIENCE treatment. Serious infusion-related reactions can happen during your infusion or within 24 hours after your infusion of RUXIENCE. Your healthcare provider should give you medicines before your infusion of RUXIENCE to decrease your chance of having a severe infusion-related reaction.
  Tell your healthcare provider or get medical help right away if you get any of these symptoms during or after an infusion of RUXIENCE:

- hives (red itchy welts) or rash
- itching
- swelling of your lips, tongue, throat or face
- sudden cough

- shortness of breath, difficulty breathing, or wheezing
- weakness
- dizziness or feel faint
- palpitations (feel like your heart is racing or fluttering)
- chest pain

- Severe skin and mouth reactions. Tell your healthcare provider or get medical help right away if you get any of these symptoms at any time during your treatment with RUXIENCE:
  - painful sores or ulcers on your skin, lips or in your mouth
  - blisters
  - peeling skin
  - rash
  - pustules
- Hepatitis B virus (HBV) reactivation. Before you receive your RUXIENCE treatment, your healthcare provider will do blood tests to check for HBV infection. If you have had hepatitis B or are a carrier of hepatitis B virus, receiving RUXIENCE could cause the virus to become an active infection again. Hepatitis B reactivation may cause serious liver problems including liver failure, and death. You should not receive RUXIENCE if you have active hepatitis B liver disease. Your healthcare provider will monitor you for hepatitis B infection during and for several months after you stop receiving RUXIENCE.
  Tell your healthcare provider right away if you get worsening tiredness, or yellowing of your skin or white part of your eyes, during treatment with RUXIENCE.
- Progressive Multifocal Leukoencephalopathy (PML). PML is a rare, serious brain infection caused by a virus that can happen in people who receive RUXIENCE. People with weakened immune systems can get PML. PML can result in death or severe disability. There is no known treatment, prevention, or cure for PML.
  Tell your healthcare provider right away if you have any new or worsening symptoms or if anyone close to you notices these symptoms:

- confusion
- dizziness or loss of balance
- difficulty walking or talking

- decreased strength or weakness on one side of your body
- vision problems

See "What are the possible side effects of RUXIENCE?" for more information about side effects.

What is RUXIENCE?
RUXIENCE is a prescription medicine used to treat:

- Adults with Non-Hodgkin's Lymphoma (NHL): alone or with other chemotherapy medicines.
- Adults with Chronic Lymphocytic Leukemia (CLL): with the chemotherapy medicines fludarabine and cyclophosphamide.
- Adults with Rheumatoid Arthritis (RA): with another prescription medicine called methotrexate, to reduce the signs and symptoms of moderate to severe active RA in adults, after treatment with at least one other medicine called a Tumor Necrosis Factor (TNF) antagonist has been used and did not work well.
- Adults with Granulomatosis with Polyangiitis (GPA) (Wegener's Granulomatosis) and Microscopic Polyangiitis (MPA): with glucocorticoids, to treat GPA and MPA.
- Adults with Pemphigus Vulgaris (PV): to treat moderate to severe PV.

RUXIENCE is not indicated for treatment of children.

Before you receive RUXIENCE, tell your healthcare provider about all of your medical conditions, including if you:

- have had a severe reaction to RUXIENCE or another rituximab product
- have a history of heart problems, irregular heart beat or chest pain
- have lung or kidney problems
- have an infection or weakened immune system
- have or have had any severe infections including:

- Hepatitis B virus (HBV)
- Hepatitis C virus (HCV)
- Cytomegalovirus (CMV)
- Herpes simplex virus (HSV)

- Parvovirus B19
- Varicella zoster virus (chickenpox or shingles)
- West Nile Virus

- have had a recent vaccination or are scheduled to receive vaccinations. You should not receive certain vaccines before or during treatment with RUXIENCE.
- are pregnant or plan to become pregnant. Talk to your healthcare provider about the risks to your unborn baby if you receive RUXIENCE during pregnancy.
  Females who are able to become pregnant:
  - Your healthcare provider should do a pregnancy test to see if you are pregnant before starting RUXIENCE.
  - You should use effective birth control (contraception) during treatment with RUXIENCE and for 12 months after your last dose of RUXIENCE. Talk to your healthcare provider about effective birth control.
  - Tell your healthcare provider right away if you become pregnant or think that you are pregnant during treatment with RUXIENCE.
- are breastfeeding or plan to breastfeed. RUXIENCE may pass into your breast milk. Do not breastfeed during treatment and for 6 months after your last dose of RUXIENCE.

Tell your healthcare provider about all the medicines you take, including prescription and over-the-counter medicines, vitamins, and herbal supplements. Especially tell your healthcare provider if you take or have taken:

- a Tumor Necrosis Factor (TNF) inhibitor medicine
- a Disease Modifying Anti-Rheumatic Drug (DMARD)

If you are not sure if your medicine is one listed above, ask your healthcare provider.

How will I receive RUXIENCE?

- RUXIENCE is given by infusion through your central catheter or through a needle placed in a vein (intravenous infusion), in your arm. Talk to your healthcare provider about how you will receive RUXIENCE.
- Your healthcare provider may prescribe medicines before each infusion of RUXIENCE to reduce infusion side effects such as fever and chills.
- Your healthcare provider should do blood tests regularly to check for side effects to RUXIENCE.
- Before each RUXIENCE treatment, your healthcare provider or nurse will ask you questions about your general health. Tell your healthcare provider or nurse about any new symptoms.

What are the possible side effects of RUXIENCE?
RUXIENCE can cause serious side effects, including:

- See "What is the most important information I should know about RUXIENCE?"
- Tumor Lysis Syndrome (TLS). TLS is caused by the fast breakdown of cancer cells. TLS can cause you to have:
  - kidney failure and the need for dialysis treatment
  - abnormal heart rhythm
TLS can happen within 12 to 24 hours after an infusion of RUXIENCE. Your healthcare provider may do blood tests to check you for TLS. Your healthcare provider may give you medicine to help prevent TLS.
  Tell your healthcare provider right away if you have any of the following signs or symptoms of TLS:

- nausea
- vomiting

- diarrhea
- lack of energy

- Serious infections. Serious infections can happen during and after treatment with RUXIENCE, and can lead to death. RUXIENCE can increase your risk of getting infections and can lower the ability of your immune system to fight infections. Types of serious infections that can happen with RUXIENCE include bacterial, fungal, and viral infections. After receiving RUXIENCE, some people have developed low levels of certain antibodies in their blood for a long period of time (longer than 11 months). Some of these people with low antibody levels developed infections. People with serious infections should not receive RUXIENCE. Tell your healthcare provider right away if you have any symptoms of infection:
  - fever
  - cold symptoms, such as runny nose or sore throat that do not go away
  - flu symptoms, such as cough, tiredness, and body aches
  - earache or headache
  - pain during urination
  - cold sores in the mouth or throat
  - cuts, scrapes or incisions that are red, warm, swollen or painful
- Heart problems. RUXIENCE may cause chest pain, irregular heartbeats, and heart attack. Your healthcare provider may monitor your heart during and after treatment with RUXIENCE if you have symptoms or heart problems or have a history of heart problems. Tell your healthcare provider right away if you have chest pain or irregular heartbeats during treatment with RUXIENCE.
- Kidney problems, especially if you are receiving RUXIENCE for NHL. RUXIENCE can cause severe kidney problems that lead to death. Your healthcare provider should do blood tests to check how well your kidneys are working.
- Stomach and Serious bowel problems that can sometimes lead to death. Bowel problems, including blockage or tears in the bowel can happen if you receive RUXIENCE with chemotherapy medicines. Tell your healthcare provider right away if you have any severe stomach-area (abdomen) pain or repeated vomiting during treatment with RUXIENCE.

Your healthcare provider will stop treatment with RUXIENCE if you have severe, serious or life-threatening side effects.
The most common side effects of RUXIENCE include:

- infusion-related reactions (see "What is the most important information I should know about RUXIENCE?")
- infections (may include fever, chills)
- body aches
- tiredness
- nausea

In adults with GPA or MPA the most common side effects of RUXIENCE also include:

- low white and red blood cells
- swelling
- diarrhea
- muscle spasms

Other side effects with RUXIENCE include:

- aching joints during or within hours of receiving an infusion
- more frequent upper respiratory tract infection

These are not all of the possible side effects with RUXIENCE.
Call your doctor for medical advice about side effects. You may report side effects to FDA at 1-800-FDA-1088.

General information about the safe and effective use of RUXIENCE.
Medicines are sometimes prescribed for purposes other than those listed in a Medication Guide. You can ask your pharmacist or healthcare provider for information about RUXIENCE that is written for healthcare providers.

What are the ingredients in RUXIENCE?
Active ingredient: rituximab-pvvr
Inactive ingredients: edetate disodium dihydrate, L-histidine, L-histidine hydrochloride monohydrate, polysorbate 80, sucrose, and Water for Injection.

Manufactured by Pfizer Ireland Pharmaceuticals, Cork, Ireland, P43 X336

U.S. License No. 2060
Distributed by Pfizer Labs Division of Pfizer Inc. New York, NY 10001
LAB-1274-6.0

For more information, go to www.pfizer.com or call 1-800-438-1985.

This Medication Guide has been approved by the U.S. Food and Drug Administration Revised: 6/2025

PRINCIPAL DISPLAY PANEL - 10 mL Vial Label

ALWAYS DISPENSE ENCLOSED
MEDICATION GUIDE TO EACH PATIENT

NDC 0069-0238-01
Rx only

Ruxience®
(rituximab-pvvr)
Injection

100 mg/10 mL
(10 mg/mL)

For Intravenous Use after dilution

ONE SINGLE-DOSE VIAL

DISCARD UNUSED PORTION.

PRINCIPAL DISPLAY PANEL - 10 mL Vial Carton

ALWAYS DISPENSE ENCLOSED
MEDICATION GUIDE TO EACH PATIENT

NDC 0069-0238-01

Ruxience®
(rituximab-pvvr)
Injection

100 mg/10 mL
(10 mg/mL)

For Intravenous Use
after dilution

ONE SINGLE-DOSE VIAL

DISCARD UNUSED PORTION.

Rx only

Pfizer Oncology

PRINCIPAL DISPLAY PANEL - 50 mL Vial Label

ALWAYS DISPENSE ENCLOSED MEDICATION GUIDE TO EACH PATIENT

NDC 0069-0249-01

Ruxience®
(rituximab-pvvr)
Injection

500 mg/50 mL
(10 mg/mL)

For Intravenous Use after dilution

ONE SINGLE-DOSE VIAL

DISCARD UNUSED PORTION.

Rx only

PRINCIPAL DISPLAY PANEL - 50 mL Vial Carton

ALWAYS DISPENSE ENCLOSED
MEDICATION GUIDE TO EACH PATIENT

NDC 0069-0249-01

Ruxience®
(rituximab-pvvr)
Injection

500 mg/50 mL
(10 mg/mL)

For Intravenous Use
after dilution

ONE SINGLE-DOSE VIAL

DISCARD UNUSED PORTION.

Rx only

Pfizer Oncology